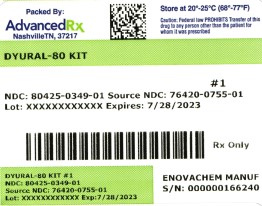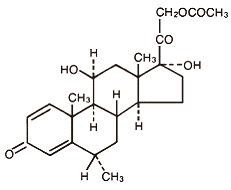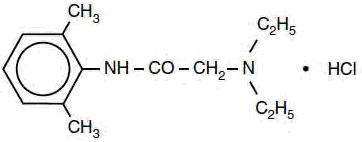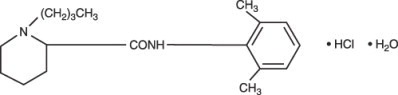 DRUG LABEL: Dyural 80 Kit
NDC: 80425-0349 | Form: KIT | Route: EPIDURAL
Manufacturer: Advanced Rx Pharmacy of Tennessee, LLC
Category: prescription | Type: HUMAN PRESCRIPTION DRUG LABEL
Date: 20241231

ACTIVE INGREDIENTS: BUPIVACAINE HYDROCHLORIDE 2.5 mg/1 mL; POVIDONE-IODINE 10 mg/1 mL; SODIUM CHLORIDE 9 mg/1 mL; WATER 1 mL/1 mL; ISOPROPYL ALCOHOL 70 mL/100 mL; METHYLPREDNISOLONE ACETATE 80 mg/1 mL; LIDOCAINE HYDROCHLORIDE 10 mg/1 mL
INACTIVE INGREDIENTS: SODIUM CHLORIDE; SODIUM HYDROXIDE; HYDROCHLORIC ACID; WATER; GLYCERIN; POLYSORBATE 80; SODIUM CITRATE; SODIUM PHOSPHATE, DIBASIC, ANHYDROUS; CITRIC ACID ACETATE; WATER; WATER; HYDROCHLORIC ACID; SODIUM HYDROXIDE; WATER; POLYETHYLENE GLYCOL 3350 28 mg/1 mL; MIRIPIRIUM CHLORIDE; SODIUM CHLORIDE; HYDROCHLORIC ACID; SODIUM HYDROXIDE; SODIUM CHLORIDE; WATER; SODIUM HYDROXIDE; HYDROCHLORIC ACID

HIGHLIGHTS OF PRESCRIBING INFORMATION

Dyural 80 Kit
These highlights do not include all the information needed to use BUPIVACAINE HYDROCHLORIDE INJECTION safely and effectively. See full prescribing information for BUPIVACAINE HYDROCHLORIDE INJECTION.
BUPIVACAINE HYDROCHLORIDE injection, for infiltration, perineural, caudal, epidural, or retrobulbar use
Initial U.S. Approval: 1972

WARNING: RISK OF CARDIAC ARREST WITH USE OF BUPIVACAINE HYDROCHLORIDE INJECTION IN OBSTETRICAL ANESTHESIA

See full prescribing information for complete boxed warning.

There have been reports of cardiac arrest with difficult resuscitation or death during use of Bupivacaine Hydrochloride Injection for epidural anesthesia in obstetrical patients. In most cases, this has followed use of the 0.75% (7.5 mg/mL) concentration. Resuscitation has been difficult or impossible despite apparently adequate preparation and appropriate management. Cardiac arrest has occurred after convulsions resulting from systemic toxicity, presumably following unintentional intravascular injection. The 0.75% (7.5 mg/mL) concentration of Bupivacaine Hydrochloride Injection is not recommended for obstetrical anesthesia and should be reserved for surgical procedures where a high degree of muscle relaxation and prolonged effect are necessary (5.1).

1 INDICATIONS AND USAGE

Bupivacaine Hydrochloride Injection contains bupivacaine, an amide local anesthetic. Bupivacaine Hydrochloride Injection is indicated in adults for the production of local or regional anesthesia or analgesia for surgery, dental and oral surgery procedures, diagnostic and therapeutic procedures, and for obstetrical procedures. For each type of block indicated to produce local or regional anesthesia or analgesia, specific concentrations and presentations are recommended. (1, 2.2)

Limitations of Use

Not all blocks are indicated for use with Bupivacaine Hydrochloride Injection given clinically significant risks associated with use. (1, 2.2, 4, 5.1, 5.4, 5.5, 5.7, 5.9)

2 DOSAGE AND ADMINISTRATION

- Not for intrathecal use. (2.1)
- Avoid use of solutions containing antimicrobial preservatives (i.e., multiple-dose vials) for epidural or caudal anesthesia. (2.1, 5.4)
- Three mL of Bupivacaine Hydrochloride and Epinephrine Injection without antimicrobial preservative (0.5% bupivacaine with 1:200,000 epinephrine) is recommended for use as a test dose prior to caudal and lumbar epidural blocks when clinical conditions permit. (2.4)
- See full prescribing information for:
  - Recommended concentrations and dosages of Bupivacaine Hydrochloride Injection/Bupivacaine Hydrochloride and Epinephrine Injection according to type of block. (2.2)
  - Additional dosage and administration information pertaining to use in epidural anesthesia, test dose for caudal and lumbar epidural blocks, use in dentistry, and use in ophthalmic surgery. (2.3, 2.4, 2.5, 2.6)

3 DOSAGE FORMS AND STRENGTHS

Bupivacaine Hydrochloride Injection, USP are available in multiple concentrations. See full prescribing information for detailed description of each formulation. (3)

4 CONTRAINDICATIONS

- Obstetrical paracervical block anesthesia. Its use in this technique has resulted in fetal bradycardia and death. (4)
- Intravenous regional anesthesia (Bier Block). (4)
- Known hypersensitivity to bupivacaine or to any local anesthetic agent of the amide-type or to other components of Bupivacaine Hydrochloride Injection/Bupivacaine Hydrochloride and Epinephrine Injection. (4)

5 WARNINGS AND PRECAUTIONS

- Dose-Related Toxicity: Monitor cardiovascular and respiratory vital signs and patient's state of consciousness after injection of Bupivacaine Hydrochloride Injection/Bupivacaine Hydrochloride and Epinephrine Injection. (5.2)
- Methemoglobinemia: Cases of methemoglobinemia have been reported in association with local anesthetic use. See full prescribing information for more detail on managing these risks. (5.3)
- Chondrolysis with Intra-Articular Infusion: Intra-articular infusions of local anesthetics including Bupivacaine Hydrochloride Injection following arthroscopic and other surgical procedures is an unapproved use, and there have been post-marketing reports of chondrolysis in patients receiving such infusions. (5.5)
- Risk of Cardiac Arrest with Intravenous Regional Anesthesia Use (Bier Block): There have been reports of cardiac arrest and death during the use of bupivacaine for intravenous regional anesthesia (Bier Block). (5.7)
- Allergic-Type Reactions to Sulfites in Bupivacaine Hydrochloride and Epinephrine Injection: Bupivacaine Hydrochloride and Epinephrine Injection contains sodium metabisulfite, a sulfite that may cause allergic-type reactions including anaphylactic symptoms and life-threatening or less severe asthmatic episodes in certain susceptible people. (5.8)
- Risk of Systemic Toxicities with Unintended Intravascular or Intrathecal Injection: Unintended intravascular or intrathecal injection may be associated with systemic toxicities, including CNS or cardiorespiratory depression and coma, progressing ultimately to respiratory arrest. Aspirate for blood or cerebrospinal fluid (where applicable) prior to each dose and consider using a test dose of Bupivacaine Hydrochloride and Epinephrine Injection. (5.9)

6 ADVERSE REACTIONS

Most common adverse reactions are related to the central nervous system and the cardiovascular system. (6)

To report SUSPECTED ADVERSE REACTIONS, contact Pfizer Inc. at 1-800-438-1985 or FDA at 1-800-FDA-1088 or www.fda.gov/medwatch.

7 DRUG INTERACTIONS

- Local Anesthetics: The toxic effects of local anesthetics are additive. Monitor for neurologic and cardiovascular effects when additional local anesthetics are administered. (7.1)
- Monoamine Oxidase Inhibitors and Tricyclic Antidepressants: Administration of Bupivacaine Hydrochloride and Epinephrine Injection to patients receiving monoamine oxidase inhibitors or tricyclic antidepressants may produce severe, prolonged hypertension. Concurrent use of these agents should generally be avoided. (5.6, 7.2)
- Ergot-Type Oxytocic Drugs: Concurrent administration of Bupivacaine Hydrochloride and Epinephrine Injection and ergot-type oxytocic drugs may cause severe, persistent hypertension or cerebrovascular accidents. (5.6, 7.3)
- Nonselective Beta-Adrenergic Antagonists: Administration of Bupivacaine Hydrochloride and Epinephrine Injection (containing a vasoconstrictor) in patients receiving nonselective beta-adrenergic antagonists may cause severe hypertension and bradycardia. Concurrent use of these agents should generally be avoided. (5.6, 7.4)
- Drugs Associated with Methemoglobinemia: Patients are at increased risk of developing methemoglobinemia when concurrently exposed to nitrates, nitrites, local anesthetics, antineoplastic agents, antibiotics, antimalarials, anticonvulsants, and other drugs. (7.5)
- Potent Inhalation Anesthetics: Serious dose-related cardiac arrhythmias may occur if preparations containing a vasoconstrictor such as epinephrine are used in patients during or following the administration of potent inhalation anesthetics. (5.13, 7.6)

8 USE IN SPECIFIC POPULATIONS

- Pediatric Use: Administration of Bupivacaine Hydrochloride Injection/Bupivacaine Hydrochloride and Epinephrine Injection in pediatric patients younger than 12 years is not recommended. (8.4)
- Geriatric Use: Patients 65 years and over, particularly those with hypertension, may be at increased risk for developing hypotension while undergoing anesthesia with Bupivacaine Hydrochloride Injection/Bupivacaine Hydrochloride and Epinephrine Injection. (8.5)
- Moderate to Severe Hepatic Impairment: Consider increased monitoring for bupivacaine systemic toxicity. (8.6)

FULL PRESCRIBING INFORMATION

WARNING: RISK OF CARDIAC ARREST WITH USE OF BUPIVACAINE HYDROCHLORIDE INJECTION IN OBSTETRICAL ANESTHESIA

There have been reports of cardiac arrest with difficult resuscitation or death during use of Bupivacaine Hydrochloride Injection for epidural anesthesia in obstetrical patients. In most cases, this has followed use of the 0.75% (7.5 mg/mL) concentration. Resuscitation has been difficult or impossible despite apparently adequate preparation and appropriate management. Cardiac arrest has occurred after convulsions resulting from systemic toxicity, presumably following unintentional intravascular injection. The 0.75% (7.5 mg/mL) concentration of Bupivacaine Hydrochloride Injection is not recommended for obstetrical anesthesia and should be reserved for surgical procedures where a high degree of muscle relaxation and prolonged effect are necessary [see Warnings and Precautions (5.1)].

1 INDICATIONS AND USAGE

Bupivacaine Hydrochloride Injection is indicated in adults for the production of local or regional anesthesia or analgesia for surgery, dental and oral surgery procedures, diagnostic and therapeutic procedures, and for obstetrical procedures. Specific concentrations and presentations of Bupivacaine Hydrochloride Injection are recommended for each type of block indicated to produce local or regional anesthesia or analgesia [see Dosage and Administration (2.2)].

Limitations of Use

Not all blocks are indicated for use with Bupivacaine Hydrochloride Injection given clinically significant risks associated with use [see Dosage and Administration (2.2), Contraindications (4), Warnings and Precautions (5.1, 5.4, 5.5, 5.7, 5.9)] .

2 DOSAGE AND ADMINISTRATION

2.1 Important Dosage and Administration Information

- Bupivacaine Hydrochloride Injection/Bupivacaine Hydrochloride and Epinephrine Injection is not for intrathecal use.
- Avoid use of Bupivacaine Hydrochloride Injection/Bupivacaine Hydrochloride and Epinephrine Injection solutions containing antimicrobial preservatives (i.e., multiple-dose vials) for epidural or caudal anesthesia [see Warnings and Precautions (5.4)] .
- Discard unused portions of solution not containing preservatives, i.e., those supplied in single-dose vials, following initial use.
- Visually inspect this product for particulate matter and discoloration prior to administration whenever solution and container permit. Bupivacaine Hydrochloride Injection/Bupivacaine Hydrochloride and Epinephrine Injection are clear, colorless solutions. Do not administer solutions which are discolored or contain particulate matter.
- Mixing or the prior or intercurrent use of any other local anesthetic with Bupivacaine Hydrochloride Injection/Bupivacaine Hydrochloride and Epinephrine Injection is not recommended because of insufficient data on the clinical use of such mixtures.

Administration Precautions

- Bupivacaine Hydrochloride Injection Injection/Bupivacaine Hydrochloride and Epinephrine Injection are to be administered in carefully adjusted dosages by or under the supervision of experienced clinicians who are well versed in the diagnosis and management of dose-related toxicity and other acute emergencies which might arise from the block to be employed.
- Use Bupivacaine Hydrochloride Injection/Bupivacaine Hydrochloride and Epinephrine Injection only if the following are immediately available: oxygen, cardiopulmonary resuscitative equipment and drugs, and the personnel resources needed for proper management of toxic reactions and related emergencies [see Warnings and Precautions (5.2), Adverse Reactions (6), Overdosage (10)] .
- The toxic effects of local anesthetics are additive. Monitor for neurologic and cardiovascular effects related to local anesthetic systemic toxicity when additional local anesthetics are administered with Bupivacaine Hydrochloride Injection/Bupivacaine Hydrochloride and Epinephrine Injection [see Warnings and Precautions (5.2), Drug Interactions (7.1), Overdosage (10)] .
- Aspirate for blood or cerebrospinal fluid (where applicable) prior to injecting Bupivacaine Hydrochloride Injection/Bupivacaine Hydrochloride and Epinephrine Injection, both the initial dose and all subsequent doses, to avoid intravascular or intrathecal injection. However, a negative aspiration for blood or cerebrospinal fluid does not ensure against an intravascular or intrathecal injection [see Warnings and Precautions (5.9)] .
- Avoid rapid injection of a large volume of Bupivacaine Hydrochloride Injection/Bupivacaine Hydrochloride and Epinephrine Injection and use fractional (incremental) doses when feasible.
- During major regional nerve blocks, such as those of the brachial plexus or lower extremity, the patient should have an indwelling intravenous catheter to assure adequate intravenous access. The lowest dosage of Bupivacaine Hydrochloride Injection/Bupivacaine Hydrochloride and Epinephrine Injection that results in effective anesthesia should be used to avoid high plasma levels and serious adverse reactions.
- Perform careful and constant monitoring of cardiovascular and respiratory (adequacy of oxygenation and ventilation) vital signs and the patient's level of consciousness after each local anesthetic injection.
- Use Bupivacaine Hydrochloride and Epinephrine Injection in carefully restricted quantities in areas of the body supplied by end arteries or having otherwise compromised blood supply such as digits, nose, external ear, or penis [see Warnings and Precautions (5.12)] .

2.2 Recommended Concentrations and Dosages of Bupivacaine Hydrochloride Injection/Bupivacaine Hydrochloride and Epinephrine Injection

The dosage of Bupivacaine Hydrochloride Injection/Bupivacaine Hydrochloride and Epinephrine Injection administered varies with the anesthetic procedure, the area to be anesthetized, the vascularity of the tissues, the number of neuronal segments to be blocked, the depth of anesthesia and degree of muscle relaxation required, the duration of anesthesia desired, individual tolerance, and the physical condition of the patient. Administer the smallest dosage and concentration required to produce the desired result.

The types of block and recommended Bupivacaine Hydrochloride Injection/Bupivacaine Hydrochloride and Epinephrine Injection concentrations are shown in Table 1.

Table 1. Types of Block and Recommended Bupivacaine Hydrochloride Injection/Bupivacaine Hydrochloride and Epinephrine Injection Concentrations
Type of Block | Bupivacaine Hydrochloride |  |  | Bupivacaine Hydrochloride and Epinephrine
Type of Block | 0.25% (2.5 mg/mL) | 0.5% (5 mg/mL) | 0.75% (7.5 mg/mL) [Bupivacaine Hydrochloride Injection 0.75% (7.5 mg/mL) is not recommended for nonobstetrical surgical procedures in pregnant patients.] | 0.25% (2.5 mg/mL) | 0.5% (5 mg/mL)
Local infiltration | ✓ |  |  | ✓
Peripheral nerve block | ✓ | ✓ |  | ✓ | ✓
Retrobulbar block |  |  | ✓
Sympathetic block | ✓
Caudal block [Avoid use of multiple-dose vials of Bupivacaine Hydrochloride Injection and Bupivacaine Hydrochloride and Epinephrine Injection for caudal or epidural anesthesia [see Warnings and Precautions (5.4)] .] | ✓ | ✓ |  | ✓ | ✓
Lumbar epidural block | ✓ | ✓ | ✓ (not for obstetrical anesthesia) | ✓ | ✓
Epidural test dose |  |  |  |  | ✓
Dental block |  |  |  |  | ✓
✓= indicated use [see Warnings and Precautions (5.1)].

At recommended dosages, Bupivacaine Hydrochloride/Bupivacaine Hydrochloride and Epinephrine produces complete sensory block, but the effect on motor function differs among the three concentrations. Table 2 provides information on the expected effect on motor function for the three concentrations.

Table 2. Bupivacaine Hydrochloride Injection/Bupivacaine Hydrochloride and Epinephrine Injection Concentration vs. Motor Function
Bupivacaine Hydrochloride Injection Concentration | Motor Function
0.25% (2.5 mg/mL) [These products include Bupivacaine Hydrochloride Injection and Bupivacaine Hydrochloride and Epinephrine Injection [the epinephrine concentration (1:200,000) is not included in the table].] | When used for caudal, epidural, or peripheral nerve block, produces incomplete motor block. Should be used for operations in which muscle relaxation is not important, or when another means of providing muscle relaxation is used concurrently. Onset of action may be slower than with the 0.5% (5 mg/mL) or 0.75% (7.5 mg/mL) solutions.
0.5% (5 mg/mL) | Provides motor blockade for caudal, epidural, or nerve block, but muscle relaxation may be inadequate for operations in which complete muscle relaxation is essential.
0.75% (7.5 mg/mL) [These are only Bupivacaine Hydrochloride Injection products [there is no 0.75% (7.5 mg/mL) concentration for Bupivacaine Hydrochloride and Epinephrine Injection].] | Produces complete motor block. Most useful for epidural block in abdominal operations requiring complete muscle relaxation, and for retrobulbar anesthesia. Not for obstetrical anesthesia.

The duration of anesthesia with Bupivacaine Hydrochloride Injection/Bupivacaine Hydrochloride and Epinephrine Injection is such that for most indications, a single-dose is sufficient.

The maximum dosage limit within the recommended dosage range must be individualized in each case after evaluating the size and physical status of the patient, as well as the anticipated rate of systemic absorption from a particular injection site.

The dosages in Table 3 are recommended as a guide for use in the average adult. These doses may be repeated once every three hours. Do not exceed a total daily dosage of 400 mg in 24 hours. The duration of anesthetic effect may be prolonged by the addition of epinephrine.

Table 3. Recommended Concentrations and Doses of Bupivacaine Hydrochloride Injection/Bupivacaine Hydrochloride and Epinephrine Injection in Adults
Type of Block | Concentration of Bupivacaine Hydrochloride Injection | Each Dose |  | Motor Block [With continuous (intermittent) techniques, repeat doses increase the degree of motor block. The first repeat dose of 0.5% (5 mg/mL) may produce complete motor block. Intercostal nerve block with 0.25% (2.5 mg/mL) also may produce complete motor block for intra-thoracic and upper intra-abdominal surgery.]
Type of Block | Concentration of Bupivacaine Hydrochloride Injection | mL | mg of Bupivacaine Hydrochloride Injection | Motor Block [With continuous (intermittent) techniques, repeat doses increase the degree of motor block. The first repeat dose of 0.5% (5 mg/mL) may produce complete motor block. Intercostal nerve block with 0.25% (2.5 mg/mL) also may produce complete motor block for intra-thoracic and upper intra-abdominal surgery.]
Local infiltration | 0.25% (2.5 mg/mL) [Solutions with or without epinephrine (i.e., applies to Bupivacaine Hydrochloride Injection and Bupivacaine Hydrochloride and Epinephrine Injection). The Bupivacaine Hydrochloride and Epinephrine Injection products include epinephrine (1:200,000).] | Up to 70 (without epinephrine) | Up to 175 (without epinephrine) | ―
Local infiltration | 0.25% (2.5 mg/mL) [Solutions with or without epinephrine (i.e., applies to Bupivacaine Hydrochloride Injection and Bupivacaine Hydrochloride and Epinephrine Injection). The Bupivacaine Hydrochloride and Epinephrine Injection products include epinephrine (1:200,000).] | Up to 90 (with epinephrine) | Up to 225 (with epinephrine) | ―
Peripheral nerve block | 0.5% (5 mg/mL) | 5–35 (without epinephrine) | 25–175 (without epinephrine) | moderate to complete
Peripheral nerve block | 0.5% (5 mg/mL) | 5–45 (with epinephrine) | 25–225 (with epinephrine) | moderate to complete
Peripheral nerve block | 0.25% (2.5 mg/mL) | 5–70 (without epinephrine) | 12.5–175 (without epinephrine) | moderate to complete
Peripheral nerve block | 0.25% (2.5 mg/mL) | 5–90 (with epinephrine) | 12.5–225 (with epinephrine) | moderate to complete
Retrobulbar block [see Dosage and Administration (2.6)] | 0.75% (7.5 mg/mL) | 2–4 | 15–30 | complete
Sympathetic block | 0.25% (2.5 mg/mL) | 20–50 | 50–125 | ―
Caudal block [see Dosage and Administration (2.4)] | 0.5% (5 mg/mL) | 15–30 | 75–150 | moderate to complete
Caudal block [see Dosage and Administration (2.4)] | 0.25% (2.5 mg/mL) | 15–30 | 37.5–75 | moderate
Lumbar epidural block [see Dosage and Administration (2.3)] | 0.75% (7.5 mg/mL) [For single-dose use; not for intermittent epidural technique. Not for obstetrical anesthesia.] | 10–20 | 75–150 | complete
Lumbar epidural block [see Dosage and Administration (2.3)] | 0.5% (5 mg/mL) | 10–20 | 50–100 | moderate to complete
Lumbar epidural block [see Dosage and Administration (2.3)] | 0.25% (2.5 mg/mL) | 10–20 | 25–50 | partial to moderate
Epidural test dose [see Dosage and Administration (2.4)] | 0.5% (5 mg/mL) with epinephrine | 2–3 | 10–15 (10–15 micrograms epinephrine) | ―
Dental [see Dosage and Administration (2.5)] | 0.5% (5 mg/mL) with epinephrine | 1.8–3.6 per site | 9–18 per site | ―

2.3 Use in Epidural Anesthesia

During the administration of epidural anesthesia, it is recommended that a test dose of Bupivacaine Hydrochloride and Epinephrine Injection without antimicrobial preservative (0.5% bupivacaine with 1:200,000 epinephrine) be administered initially and the effects monitored before the full dose is given. When using a "continuous" catheter technique, test doses should be given prior to both the initial and all supplemental doses, because a catheter in the epidural space can migrate into a blood vessel or through the dura [see Dosage and Administration (2.4)] .

During epidural administration, administer Bupivacaine Hydrochloride Injection/Bupivacaine Hydrochloride and Epinephrine Injection, 0.5% (5 mg/mL) and Bupivacaine Hydrochloride Injection 0.75% (7.5 mg/mL) solutions in incremental doses of 3 mL to 5 mL with sufficient time between doses to detect toxic manifestations of unintentional intravascular or intrathecal injection. Administer injections slowly, with frequent aspirations before and during the injection to avoid intravascular injection. Perform syringe aspirations before and during each supplemental injection in continuous (intermittent) catheter techniques. In obstetrics, use ONLY the 0.5% (5 mg/mL) and 0.25% (2.5 mg/mL) concentrations of Bupivacaine Hydrochloride Injection/Bupivacaine Hydrochloride and Epinephrine Injection [see Warnings and Precautions (5.1)]; incremental doses of 3 mL to 5 mL of the 0.5% (5 mg/mL) solution not exceeding 50 mg to 100 mg at any dosing interval are recommended. Repeat doses should be preceded by a test dose containing epinephrine if not clinically contraindicated. Use only the single-dose vials for caudal or epidural anesthesia; avoid use of the multiple-dose vials for these procedures, which contain a preservative [see Dosage and Administration (2.1, 2.4), Warnings and Precautions (5.4, 5.9)] .

2.4 Test Dose for Caudal and Lumbar Epidural Blocks

Three mL of Bupivacaine Hydrochloride and Epinephrine Injection without antimicrobial preservative (0.5% bupivacaine with 1:200,000 epinephrine) is recommended for use as a test dose prior to caudal and lumbar epidural blocks when clinical conditions permit. This test dose may serve as a warning of unintended intravascular or intrathecal injection. Closely monitor for early clinical signs of toxicity following each test dose [see Warnings and Precautions (5.9)] . Allot adequate time for onset of spinal block to detect possible intrathecal injection. An intravascular or intrathecal injection is still possible even if results of the test dose are negative. The test dose itself may produce a systemic toxic reaction, high spinal, or cardiovascular effects from the epinephrine [see Warnings and Precautions (5.2, 5.9), Overdosage (10)].

2.5 Use in Dentistry

Bupivacaine Hydrochloride and Epinephrine Injection 0.5% (5 mg/mL) is recommended for infiltration and block injection in the maxillary and mandibular area when a longer duration of local anesthesia is desired, such as for procedures generally associated with significant postoperative pain. The average dose of 1.8 mL (9 mg) per injection site will usually suffice; an occasional second dose of 1.8 mL (9 mg) may be used if necessary to produce adequate anesthesia after allowing 2 to 10 minutes for block onset [see Clinical Pharmacology (12.2)]. Use the lowest effective dose and allow time between injections; it is recommended that the total dose for all injection sites, spread out over a single dental sitting, not exceed 90 mg for a healthy adult patient (ten 1.8 mL injections of 0.5% (5 mg/mL) Bupivacaine Hydrochloride and Epinephrine Injection). Inject slowly and with frequent aspirations.

2.6 Use in Ophthalmic Surgery

When Bupivacaine Hydrochloride Injection 0.75% (7.5 mg/mL) is used for retrobulbar block, complete corneal anesthesia usually precedes onset of clinically acceptable external ocular muscle akinesia. Therefore, presence of akinesia rather than anesthesia alone should determine readiness of the patient for surgery [see Warnings and Precautions (5.15)] .

3 DOSAGE FORMS AND STRENGTHS

Bupivacaine Hydrochloride Injection, USP is a clear, colorless solution available as:

- 0.25% (25 mg/10 mL) (2.5 mg/mL) in single-dose teartop vials.
- 0.25% (75 mg/30 mL) (2.5 mg/mL) in single-dose teartop vials.
- 0.25% (125 mg/50 mL) (2.5 mg/mL) in multiple-dose fliptop vials.

- 0.5% (50 mg/10 mL) (5 mg/mL) in single-dose teartop vials.
- 0.5% (150 mg/30 mL) (5 mg/mL) in single-dose teartop vials.
- 0.5% (250 mg/50 mL) (5 mg/mL) in multiple-dose fliptop vials.

- 0.75% (75 mg/10 mL) (7.5 mg/mL) in single-dose teartop vials.
- 0.75% (225 mg/30 mL) (7.5 mg/mL) in single-dose teartop vials.

4 CONTRAINDICATIONS

Bupivacaine Hydrochloride Injection/Bupivacaine Hydrochloride and Epinephrine Injection is contraindicated in:

- obstetrical paracervical block anesthesia. Its use in this technique has resulted in fetal bradycardia and death.
- intravenous regional anesthesia (Bier Block) [see Warnings and Precautions (5.7)].
- patients with a known hypersensitivity to bupivacaine or to any local anesthetic agent of the amide-type or to other components of Bupivacaine Hydrochloride Injection/Bupivacaine Hydrochloride and Epinephrine Injection.

5 WARNINGS AND PRECAUTIONS

5.1 Risk of Cardiac Arrest with Use of Bupivacaine Hydrochloride Injection in Obstetrical Anesthesia

There have been reports of cardiac arrest with difficult resuscitation or death during use of Bupivacaine Hydrochloride Injection for epidural anesthesia in obstetrical patients. In most cases, this has followed use of the 0.75% (7.5 mg/mL) concentration. Resuscitation has been difficult or impossible despite apparently adequate preparation and appropriate management. Cardiac arrest has occurred after convulsions resulting from systemic toxicity, presumably following unintentional intravascular injection. The 0.75% (7.5 mg/mL) concentration of Bupivacaine Hydrochloride Injection is not recommended for obstetrical anesthesia and should be reserved for surgical procedures where a high degree of muscle relaxation and prolonged effect are necessary.

5.2 Dose-Related Toxicity

The safety and effectiveness of Bupivacaine Hydrochloride Injection/Bupivacaine Hydrochloride and Epinephrine Injection depend on proper dosage, correct technique, adequate precautions, and readiness for emergencies. Careful and constant monitoring of cardiovascular and respiratory (adequacy of ventilation) vital signs and the patient's state of consciousness should be performed after injection of Bupivacaine Hydrochloride Injection/Bupivacaine Hydrochloride and Epinephrine Injection solutions.

Possible early warning signs of central nervous system (CNS) toxicity are restlessness, anxiety, incoherent speech, lightheadedness, numbness and tingling of the mouth and lips, metallic taste, tinnitus, dizziness, blurred vision, tremors, twitching, CNS depression, or drowsiness. Delay in proper management of dose-related toxicity, underventilation from any cause, and/or altered sensitivity may lead to the development of acidosis, cardiac arrest, and, possibly, death.

During major regional nerve blocks, such as those of the brachial plexus or lower extremity, the patient should have an indwelling intravenous catheter to assure adequate intravenous access. Use the lowest dosage of Bupivacaine Hydrochloride Injection/Bupivacaine Hydrochloride and Epinephrine Injection that results in effective anesthesia to avoid high plasma levels and serious adverse effects. Avoid rapid injection of a large volume of Bupivacaine. Hydrochloride Injection/Bupivacaine Hydrochloride and Epinephrine Injection solution and administer fractional (incremental) doses when feasible.

Injection of repeated doses of Bupivacaine Hydrochloride Injection/Bupivacaine Hydrochloride and Epinephrine Injection may cause significant increases in plasma levels with each repeated dose due to slow accumulation of the drug or its metabolites, or to slow metabolic degradation. Tolerance to elevated blood levels varies with the status of the patient. Debilitated, elderly patients and acutely ill patients should be given reduced doses commensurate with their age and physical status.

5.3 Methemoglobinemia

Cases of methemoglobinemia have been reported in association with local anesthetic use. Although all patients are at risk for methemoglobinemia, patients with glucose-6-phosphate dehydrogenase deficiency, congenital or idiopathic methemoglobinemia, cardiac or pulmonary compromise, infants under 6 months of age, and concurrent exposure to oxidizing agents or their metabolites are more susceptible to developing clinical manifestations of the condition [see Drug Interactions (7.5)] . If local anesthetics must be used in these patients, close monitoring for symptoms and signs of methemoglobinemia is recommended.

Signs of methemoglobinemia may occur immediately or may be delayed some hours after exposure, and are characterized by a cyanotic skin discoloration and/or abnormal coloration of the blood. Methemoglobin levels may continue to rise; therefore, immediate treatment is required to avert more serious CNS and cardiovascular adverse effects, including seizures, coma, arrhythmias, and death. Discontinue Bupivacaine Hydrochloride Injection/Bupivacaine Hydrochloride and Epinephrine Injection and any other oxidizing agents. Depending on the severity of the signs and symptoms, patients may respond to supportive care, i.e., oxygen therapy, hydration. A more severe clinical presentation may require treatment with methylene blue, exchange transfusion, or hyperbaric oxygen.

5.4 Antimicrobial Preservatives in Multiple-Dose Vials

Avoid use of Bupivacaine Hydrochloride Injection/Bupivacaine Hydrochloride and Epinephrine Injection solutions containing antimicrobial preservatives, i.e., those supplied in multiple-dose vials, for epidural or caudal anesthesia because safety has not been established with such use.

5.5 Chondrolysis with Intra-Articular Infusion

Intra-articular infusions of local anesthetics including Bupivacaine Hydrochloride Injection following arthroscopic and other surgical procedures is an unapproved use, and there have been post-marketing reports of chondrolysis in patients receiving such infusions. The majority of reported cases of chondrolysis have involved the shoulder joint; cases of gleno-humeral chondrolysis have been described in pediatric and adult patients following intra-articular infusions of local anesthetics with and without epinephrine for periods of 48 to 72 hours. There is insufficient information to determine whether shorter infusion periods are associated with chondrolysis. The time of onset of symptoms, such as joint pain, stiffness and loss of motion can be variable, but may begin as early as the 2ndmonth after surgery. Currently, there is no effective treatment for chondrolysis; patients who experienced chondrolysis have required additional diagnostic and therapeutic procedures and some required arthroplasty or shoulder replacement.

5.6 Risk of Adverse Reactions Due to Drug Interactions with Bupivacaine Hydrochloride and Epinephrine Injection

Risk of Severe, Persistent Hypertension Due to Drug Interactions Between Bupivacaine Hydrochloride and Epinephrine Injection and Monoamine Oxidase Inhibitors and Tricyclic Antidepressants

Administration of Bupivacaine Hydrochloride and Epinephrine Injection (containing a vasoconstrictor) in patients receiving monoamine oxidase inhibitors (MAOI), or tricyclic antidepressants may result in severe, prolonged hypertension. Concurrent use of these agents should generally be avoided. In situations when concurrent therapy is necessary, careful monitoring of the patient's hemodynamic status is essential [see Drug Interactions (7.2)].

Risk of Severe, Persistent Hypertension or Cerebrovascular Accidents Due to Drug Interactions Between Bupivacaine Hydrochloride and Epinephrine Injection and Ergot-Type Oxytocic Drugs

Concurrent administration of Bupivacaine Hydrochloride and Epinephrine Injection and ergot-type oxytocic drugs may cause severe, persistent hypertension or cerebrovascular accidents. Avoid use of Bupivacaine Hydrochloride and Epinephrine Injection concomitantly with ergot-type oxytocic drugs [see Drug Interactions (7.3)] .

Risk of Hypertension and Bradycardia Due to Drug Interactions Between Bupivacaine Hydrochloride and Epinephrine Injection and Nonselective Beta-Adrenergic Antagonists

Administration of Bupivacaine Hydrochloride and Epinephrine Injection (containing a vasoconstrictor) in patients receiving nonselective beta-adrenergic antagonists may cause severe hypertension and bradycardia. Concurrent use of these agents should generally be avoided. In situations when concurrent therapy is necessary, careful monitoring of the patient's blood pressure and heart rate is essential [see Drug Interactions (7.4)] .

5.7 Risk of Cardiac Arrest with Intravenous Regional Anesthesia Use (Bier Block)

There have been reports of cardiac arrest and death during the use of bupivacaine for intravenous regional anesthesia (Bier Block). Information on safe dosages and techniques of administration of Bupivacaine Hydrochloride Injection in this procedure is lacking. Therefore, Bupivacaine Hydrochloride Injection/Bupivacaine Hydrochloride and Epinephrine Injection is contraindicated for use with this technique [see Contraindications (4)] .

5.8 Allergic-Type Reactions to Sulfites in Bupivacaine Hydrochloride and Epinephrine Injection

Bupivacaine Hydrochloride and Epinephrine Injection contains sodium metabisulfite, a sulfite that may cause allergic-type reactions including anaphylactic symptoms and life-threatening or less severe asthmatic episodes in certain susceptible people. The overall prevalence of sulfite sensitivity in the general population is unknown and probably low. Sulfite sensitivity is seen more frequently in asthmatic than in nonasthmatic people. Bupivacaine Hydrochloride Injection without epinephrine does not contain sodium metabisulfite.

5.9 Risk of Systemic Toxicities with Unintended Intravascular or Intrathecal Injection

Unintended intravascular or intrathecal injection of. Bupivacaine Hydrochloride Injection/Bupivacaine Hydrochloride and Epinephrine Injection may be associated with systemic toxicities, including CNS or cardiorespiratory depression and coma, progressing ultimately to respiratory arrest. Unintentional intrathecal injection during the intended performance of caudal or lumbar epidural block or nerve blocks near the vertebral column has resulted in underventilation or apnea ("Total or High Spinal"). A high spinal has been characterized by paralysis of the legs, loss of consciousness, respiratory paralysis, and bradycardia [see Adverse Reactions (6)] .

Aspirate for blood or cerebrospinal fluid (where applicable) before injecting Bupivacaine Hydrochloride Injection/Bupivacaine Hydrochloride and Epinephrine Injection, both the initial dose and all subsequent doses, to avoid intravascular or intrathecal injection. However, a negative aspiration for blood or cerebrospinal fluid does not ensure against an intravascular or intrathecal injection.

Use of Test Dose with Epidural Anesthesia

To serve as a warning of unintended intravascular or intrathecal injection, 3 mL of Bupivacaine Hydrochloride and Epinephrine Injection without antimicrobial preservative (0.5% bupivacaine with 1:200,000 epinephrine) may be used as a test dose prior to administration of the full dose in caudal and lumbar epidural blocks [see Dosage and Administration (2.4)] . Three mL of Bupivacaine Hydrochloride and Epinephrine Injection without antimicrobial preservative (0.5% bupivacaine with 1:200,000 epinephrine) contains 15 mg bupivacaine and 15 mcg epinephrine. An intravascular or intrathecal injection is still possible even if results of the test dose are negative.

Signs/symptoms of unintended intravascular or intrathecal injection of the test dose of Bupivacaine Hydrochloride and Epinephrine Injection and monitoring recommendations are described below.

- Unintended intravascularinjection: Likely to produce a transient "epinephrine response" within 45 seconds, consisting of an increase in heart rate and/or systolic blood pressure, circumoral pallor, palpitations, and nervousness in the unsedated patient. The sedated patient may exhibit only a pulse rate increase of 20 or more beats per minute for 15 or more seconds. Therefore, following the test dose, the heart rate should be monitored for increases. Patients on beta-blockers may not manifest changes in heart rate, but blood pressure monitoring can detect a transient rise in systolic blood pressure.
- Unintended intrathecalinjection: Evidenced within a few minutes by signs of spinal block (e.g., decreased sensation of the buttocks, paresis of the legs, or, in the sedated patient, absent knee jerk).

The test dose itself may produce a systemic toxic reaction, high spinal or epinephrine-induced cardiovascular effects [see Overdosage (10)] .

5.10 Risk of Toxicity in Patients with Hepatic Impairment

Because amide local anesthetics such as bupivacaine are metabolized by the liver, consider reduced dosing and increased monitoring for bupivacaine systemic toxicity in patients with moderate to severe hepatic impairment who are treated Bupivacaine Hydrochloride Injection/Bupivacaine Hydrochloride and Epinephrine Injection, especially with repeat doses [see Use in Specific Populations (8.6)].

5.11 Risk of Use in Patients with Impaired Cardiovascular Function

Bupivacaine Hydrochloride Injection/Bupivacaine Hydrochloride and Epinephrine Injection should be given in reduced doses in patients with impaired cardiovascular function (e.g., hypotension, heartblock) because they may be less able to compensate for functional changes associated with the prolongation of AV conduction produced by Bupivacaine Hydrochloride Injection/Bupivacaine Hydrochloride and Epinephrine Injection. Monitor patients closely for blood pressure, heart rate, and ECG changes.

5.12 Risk of Ischemic Injury or Necrosis in Body Areas with Limited Blood Supply

Use Bupivacaine Hydrochloride and Epinephrine Injection in carefully restricted quantities in areas of the body supplied by end arteries or having otherwise compromised blood supply such as digits, nose, external ear, or penis. Patients with hypertensive vascular disease may exhibit exaggerated vasoconstrictor response. Ischemic injury or necrosis may result.

5.13 Risk of Cardiac Arrhythmias with Concomitant Use of Potent Inhalation Anesthetics

Serious dose-related cardiac arrhythmias may occur if preparations containing a vasoconstrictor such as epinephrine (e.g., Bupivacaine Hydrochloride and Epinephrine Injection) are used in patients during or following the administration of potent inhalation anesthetics [see Drug Interactions (7.6)] . In deciding whether to concurrently use Bupivacaine Hydrochloride and Epinephrine Injection with potent inhalation anesthetics in the same patient, the combined action of both agents upon the myocardium, the concentration and volume of vasoconstrictor used, and the time since injection, when applicable, should be taken into account.

5.14 Risk of Adverse Reactions with Use in Head and Neck Area

Small doses of local anesthetics (e.g., Bupivacaine Hydrochloride Injection) injected into the head and neck area, including retrobulbar, dental, and stellate ganglion blocks, may produce adverse reactions similar to systemic toxicity seen with unintentional intravascular injections of larger doses. The injection procedures require the utmost care. Confusion, convulsions, respiratory depression, and/or respiratory arrest, and cardiovascular stimulation or depression have been reported. These reactions may be due to intra-arterial injection of the local anesthetic with retrograde flow to the cerebral circulation. They may also be due to puncture of the dural sheath of the optic nerve during retrobulbar block with diffusion of any local anesthetic along the subdural space to the midbrain. Monitor circulation and respiration and constantly observe patients receiving Bupivacaine Hydrochloride Injection/Bupivacaine Hydrochloride and Epinephrine Injection blocks. Resuscitative equipment and drugs, and personnel for treating adverse reactions should be immediately available. Dosage recommendations should not be exceeded [see Dosage and Administration (2.2)].

5.15 Risk of Respiratory Arrest with Use in Ophthalmic Surgery

Clinicians who perform retrobulbar blocks should be aware that there have been reports of respiratory arrest following local anesthetic injection. Prior to retrobulbar block (e.g., with Bupivacaine Hydrochloride Injection/Bupivacaine Hydrochloride and Epinephrine Injection), as with all other regional procedures, resuscitative equipment and drugs, and personnel to manage respiratory arrest or depression, convulsions, and cardiac stimulation or depression should be immediately available [see Warnings and Precautions (5.14)]. As with other anesthetic procedures, patients should be constantly monitored following ophthalmic blocks for signs of these adverse reactions, which may occur following relatively low total doses.

A concentration of 0.75% bupivacaine is indicated for retrobulbar block; however, this concentration is not indicated for any other peripheral nerve block, including the facial nerve, and not indicated for local infiltration, including the conjunctiva [see Indications and Usage (1)].

5.16 Risk of Inadvertent Trauma to Tongue, Lips, and Buccal Mucosa in Dental Applications

Because of the long duration of anesthesia, when Bupivacaine Hydrochloride and Epinephrine Injection [0.5% (5 mg/mL) of bupivacaine] is used for dental injections, warn patients about the possibility of inadvertent trauma to tongue, lips, and buccal mucosa and advise them not to chew solid foods until sensation returns [see Patient Counseling Information (17)] .

6 ADVERSE REACTIONS

The following clinically significant adverse reactions have been reported and described in the Warnings and Precautions section of the labeling:

- Cardiac Arrest in Obstetrical Anesthesia [see Warnings and Precautions (5.1)]
- Dose-Related Toxicity [see Warnings and Precautions (5.2)]
- Methemoglobinemia [see Warnings and Precautions (5.3)]
- Chondrolysis with Intra-Articular Infusion [see Warnings and Precautions (5.5)]
- Severe, Persistent Hypertension, Cerebrovascular Accidents, and Bradycardia Due to Drug Interactions [see Warnings and Precautions (5.6)]
- Cardiac Arrest with Intravenous Regional Anesthesia Use [see Contraindications (4), Warnings and Precautions (5.7)]
- Allergic-Type Reactions [see Warnings and Precautions (5.8)]
- Systemic Toxicities with Unintended Intravascular or Intrathecal Injection [see Warnings and Precautions (5.9)]
- Respiratory Arrest Following Retrobulbar Block [see Warnings and Precautions (5.15)]

The following adverse reactions from voluntary reports or clinical studies have been reported with bupivacaine or bupivacaine and epinephrine. Because many of these reactions were reported voluntarily from a population of uncertain size, it is not always possible to reliably estimate their frequency or establish a causal relationship to drug exposure.

Adverse reactions to Bupivacaine Hydrochloride Injection/Bupivacaine Hydrochloride and Epinephrine Injection are characteristic of those associated with other amide-type local anesthetics. A major cause of adverse reactions to this group of drugs is excessive plasma levels, which may be due to overdosage, unintentional intravascular injection, or slow metabolic degradation.

The most commonly encountered acute adverse reactions that demand immediate counter-measures were related to the CNS and the cardiovascular system. These adverse reactions were generally dose-related and due to high plasma levels which may have resulted from overdosage, rapid absorption from the injection site, diminished tolerance, or from unintentional intravascular injection of the local anesthetic solution. In addition to systemic dose-related toxicity, unintentional intrathecal injection of drug during the intended performance of caudal or lumbar epidural block or nerve blocks near the vertebral column (especially in the head and neck region) has resulted in underventilation or apnea ("Total or High Spinal"). Also, hypotension due to loss of sympathetic tone and respiratory paralysis or underventilation due to cephalad extension of the motor level of anesthesia have occurred. This has led to secondary cardiac arrest when untreated.

Nervous System Disorders

Adverse reactions were characterized by excitation and/or depression of the central nervous system and included restlessness, anxiety, dizziness, tinnitus, blurred vision, tremors, convulsions, drowsiness, unconsciousness, respiratory arrest, nausea, vomiting, chills, pupillary constriction.

In the practice of caudal or lumbar epidural block, unintentional penetration of the subarachnoid space by the catheter or needle has occurred. Subsequent adverse effects may have depended partially on the amount of drug administered intrathecally and the physiological and physical effects of a dural puncture. A high spinal has been characterized by paralysis of the legs, loss of consciousness, respiratory paralysis, and bradycardia.

Neurologic effects following epidural or caudal anesthesia have included spinal block of varying magnitude (including high or total spinal block); hypotension secondary to spinal block; urinary retention; fecal and urinary incontinence; loss of perineal sensation and sexual function; persistent anesthesia, paresthesia, weakness, paralysis of the lower extremities and loss of sphincter control, all of which had slow, incomplete, or no recovery; headache; backache; septic meningitis; meningismus; slowing of labor; increased incidence of forceps delivery; and cranial nerve palsies due to traction on nerves from loss of cerebrospinal fluid.

Neurologic effects following other procedures or routes of administration have included persistent anesthesia, paresthesia, weakness, paralysis, all with slow, incomplete, or no recovery.

Convulsions: Incidence varied with the procedure used and the total dose administered. In a survey of studies of epidural anesthesia, overt toxicity progressing to convulsions occurred in approximately 0.1% of local anesthetic administrations. The incidences of adverse neurologic reactions associated with the use of local anesthetics may be related to the total dose of local anesthetic administered and are also dependent upon the particular drug used, the route of administration, and the physical status of the patient.

Cardiac Disorders

High doses or unintentional intravascular injection have led to high plasma levels and related depression of the myocardium, decreased cardiac output, heartblock, hypotension, bradycardia, ventricular arrhythmias, including ventricular tachycardia and ventricular fibrillation, and cardiac arrest [see Warnings and Precautions (5.9)].

Immune System Disorders

Allergic-type reactions have occurred as a result of sensitivity to bupivacaine or to other formulation ingredients, such as the antimicrobial preservative methylparaben contained in multiple-dose vials or sulfites in epinephrine-containing solutions. These reactions were characterized by signs such as urticaria, pruritus, erythema, angioneurotic edema (including laryngeal edema), tachycardia, sneezing, nausea, vomiting, dizziness, syncope, excessive sweating, elevated temperature, and severe hypotension. Cross sensitivity among members of the amide-type local anesthetic group has been reported [see Warnings and Precautions (5.8)] .

7 DRUG INTERACTIONS

7.1 Local Anesthetics

The toxic effects of local anesthetics are additive. If coadministration of other local anesthetics with Bupivacaine Hydrochloride Injection/Bupivacaine Hydrochloride and Epinephrine Injection cannot be avoided, monitor patients for neurologic and cardiovascular effects related to local anesthetic systemic toxicity [see Dosage and Administration (2.1), Warnings and Precautions (5.2)] .

7.2 Monoamine Oxidase Inhibitors and Tricyclic Antidepressants

The administration Bupivacaine Hydrochloride and Epinephrine Injection to patients receiving monoamine oxidase inhibitors, or tricyclic antidepressants may produce severe, prolonged hypertension. Concurrent use of these agents should generally be avoided. In situations when concurrent therapy is necessary, careful monitoring of the patient's hemodynamic status is essential [see Warnings and Precautions (5.6)] .

7.3 Ergot-Type Oxytocic Drugs

Concurrent administration of Bupivacaine Hydrochloride and Epinephrine Injection and ergot-type oxytocic drugs may cause severe, persistent hypertension or cerebrovascular accidents. Avoid use of Bupivacaine Hydrochloride and Epinephrine concomitantly with ergot-type oxytocic drugs [see Warnings and Precautions (5.6)].

7.4 Nonselective Beta-Adrenergic Antagonists

Administration of Bupivacaine Hydrochloride and Epinephrine Injection (containing a vasoconstrictor) in patients receiving nonselective beta-adrenergic antagonists may cause severe hypertension and bradycardia. Concurrent use of these agents should generally be avoided. In situations when concurrent therapy is necessary, careful monitoring of the patient's blood pressure and heart rate is essential [see Warnings and Precautions (5.6)].

7.5 Drugs Associated with Methemoglobinemia

Patients who are administered Bupivacaine Hydrochloride Injection/Bupivacaine Hydrochloride and Epinephrine Injection are at increased risk of developing methemoglobinemia when concurrently exposed to following drugs, which could include other local anesthetics [see Warnings and Precautions (5.3)] .

Examples of Drugs Associated with Methemoglobinemia:
Class | Examples
Nitrates/Nitrites | nitric oxide, nitroglycerin, nitroprusside, nitrous oxide
Local anesthetics | articaine, benzocaine, bupivacaine, lidocaine, mepivacaine, prilocaine, procaine, ropivacaine, tetracaine
Antineoplastic agents | cyclophosphamide, flutamide, hydroxyurea, isofamide, rasburicase
Antibiotics | dapsone, nitrofurantoin, para-aminosalicylic acid, sulfonamides
Antimalarials | chloroquine, primaquine
Anticonvulsants | phenobarbital, phenytoin, sodium valproate
Other drugs | acetaminophen, metoclopramide, quinine, sulfasalazine

7.6 Potent Inhalation Anesthetics

Serious dose-related cardiac arrhythmias may occur if preparations containing a vasoconstrictor such as epinephrine (e.g., Bupivacaine Hydrochloride and Epinephrine Injection) are used in patients during or following the administration of potent inhalation anesthetics [see Warnings and Precautions (5.13)] .

7.7 Phenothiazines and Butyrophenones

Phenothiazines and butyrophenones may reduce or reverse the pressor effect of epinephrine. Concurrent use of Bupivacaine Hydrochloride and Epinephrine Injection and these agents should generally be avoided. In situations when concurrent therapy is necessary, careful patient monitoring is essential.

8 USE IN SPECIFIC POPULATIONS

8.1 Pregnancy

Risk Summary

Bupivacaine Hydrochloride Injection/Bupivacaine Hydrochloride and Epinephrine Injection is contraindicated for obstetrical paracervical block anesthesia. Its use in this technique has resulted in fetal bradycardia and death [see Contraindications (4), Warnings and Precautions (5.1)].

There are no available data on use of Bupivacaine Hydrochloride Injection/Bupivacaine Hydrochloride and Epinephrine Injection in pregnant women to inform a drug-associated risk of adverse developmental outcomes.

In animal studies, embryo-fetal lethality was noted when bupivacaine was administered subcutaneously to pregnant rabbits during organogenesis at clinically relevant doses. Decreased pup survival was observed in a rat pre- and post-natal developmental study (dosing from implantation through weaning) at a dose level comparable to the daily maximum recommended human dose (MRHD) on a body surface area (BSA) basis. Based on animal data, advise pregnant women of the potential risks to a fetus (see Data).

Local anesthetics rapidly cross the placenta, and when used for epidural, caudal, or pudendal block anesthesia, can cause varying degrees of maternal, fetal, and neonatal toxicity [see Clinical Pharmacology (12.3)]. The incidence and degree of toxicity depend upon the procedure performed, the type, and amount of drug used, and the technique of drug administration. Adverse reactions in the parturient, fetus, and neonate involve alterations of the CNS, peripheral vascular tone, and cardiac function.

If this drug is used during pregnancy, or if the patient becomes pregnant while taking this drug, inform the patient of the potential hazard to the fetus. The estimated background risk of major birth defects and miscarriage for the indicated populations are unknown. In the U.S. general population, the estimated background risk of major birth defects and miscarriage in clinically recognized pregnancies is 2–4% and 15–20%, respectively.

Clinical Considerations

Maternal Adverse Reactions

Maternal hypotension has resulted from regional anesthesia. Local anesthetics produce vasodilation by blocking sympathetic nerves. The supine position is dangerous in pregnant women at term because of aortocaval compression by the gravid uterus. Therefore, during treatment of systemic toxicity, maternal hypotension or fetal bradycardia following regional block, the parturient should be maintained in the left lateral decubitus position if possible, or manual displacement of the uterus off the great vessels be accomplished. Elevating the patient's legs will also help prevent decreases in blood pressure. The fetal heart rate also should be monitored continuously and electronic fetal monitoring is highly advisable.

Labor or Delivery

Epidural, caudal, or pudendal anesthesia may alter the forces of parturition through changes in uterine contractility or maternal expulsive efforts. Epidural anesthesia has been reported to prolong the second stage of labor by removing the parturient's reflex urge to bear down or by interfering with motor function. The use of obstetrical anesthesia may increase the need for forceps assistance.

The use of some local anesthetic drug products during labor and delivery may be followed by diminished muscle strength and tone for the first day or two of life. This has not been reported with bupivacaine.

It is extremely important to avoid aortocaval compression by the gravid uterus during administration of regional block to parturients. To do this, the patient must be maintained in the left lateral decubitus position or a blanket roll or sandbag may be placed beneath the right hip and gravid uterus displaced to the left.

Data

Animal Data

Bupivacaine hydrochloride produced developmental toxicity when administered subcutaneously to pregnant rats and rabbits at clinically relevant doses.

Bupivacaine hydrochloride was administered subcutaneously to rats at doses of 4.4, 13.3, & 40 mg/kg and to rabbits at doses of 1.3, 5.8, & 22.2 mg/kg during the period of organogenesis (implantation to closure of the hard palate). The high doses are comparable to the daily MRHD of 400 mg/day on a mg/m^2BSA basis. No embryo-fetal effects were observed in rats at the high dose which caused increased maternal lethality. An increase in embryo-fetal deaths was observed in rabbits at the high dose in the absence of maternal toxicity with the fetal No Observed Adverse Effect Level representing approximately 0.3 times the MRHD on a BSA basis.

In a rat pre-and post-natal developmental study (dosing from implantation through weaning) conducted at subcutaneous doses of 4.4, 13.3, & 40 mg/kg, decreased pup survival was observed at the high dose. The high dose is comparable to the daily MRHD of 400 mg/day on a BSA basis.

8.2 Lactation

Risk Summary

Lactation studies have not been conducted with bupivacaine. Bupivacaine has been reported to be excreted in human milk suggesting that the nursing infant could be theoretically exposed to a dose of the drug. Bupivacaine Hydrochloride Injection/Bupivacaine Hydrochloride and Epinephrine Injection should be administered to lactating women only if clearly indicated. Studies assessing the effects of Bupivacaine Hydrochloride Injection/Bupivacaine Hydrochloride and Epinephrine Injection in breastfed children have not been performed. Studies to assess the effect of Bupivacaine Hydrochloride Injection/Bupivacaine Hydrochloride and Epinephrine Injection on milk production or excretion have not been performed. The developmental and health benefits of breastfeeding should be considered along with the mother's clinical need for bupivacaine and any potential adverse effects on the breastfed child from bupivacaine or from the underlying maternal condition.

8.4 Pediatric Use

Bupivacaine Hydrochloride Injection/Bupivacaine Hydrochloride and Epinephrine Injection is approved for use in adults. Administration of Bupivacaine Hydrochloride Injection/Bupivacaine Hydrochloride and Epinephrine Injection in pediatric patients younger than 12 years is not recommended.

Continuous infusions of bupivacaine in pediatric patients have been reported to result in high systemic levels of bupivacaine and seizures; high plasma levels may also be associated with cardiovascular abnormalities.

8.5 Geriatric Use

Patients 65 years and over, particularly those with hypertension, may be at increased risk for developing hypotension while undergoing anesthesia with Bupivacaine Hydrochloride Injection/Bupivacaine Hydrochloride and Epinephrine Injection.

In clinical studies of bupivacaine, elderly patients reached the maximal spread of analgesia and maximal motor blockade more rapidly than younger adult patients.

Differences in various pharmacokinetic parameters have been observed between elderly and younger adult patients [see Clinical Pharmacology (12.3)].

This product is known to be substantially excreted by the kidney, and the risk of adverse reactions to this drug may be greater in patients with impaired renal function. Because elderly patients are more likely to have decreased renal function, care should be taken in dose selection, and it may be useful to monitor renal function. Elderly patients may require lower doses of Bupivacaine Hydrochloride Injection/Bupivacaine Hydrochloride and Epinephrine Injection.

8.6 Hepatic Impairment

Amide-type local anesthetics, such as bupivacaine, are metabolized by the liver. Patients with severe hepatic impairment, because of their inability to metabolize local anesthetics normally, are at a greater risk of developing toxic plasma concentrations, and potentially local anesthetic systemic toxicity. Therefore, consider reduced dosing and increased monitoring for local anesthetic systemic toxicity in patients with moderate to severe hepatic impairment treated with Bupivacaine Hydrochloride Injection/Bupivacaine Hydrochloride and Epinephrine Injection, especially with repeat doses [see Warnings and Precautions (5.10)] .

8.7 Renal Impairment

Bupivacaine is known to be substantially excreted by the kidney, and the risk of adverse reactions to this drug may be greater in patients with renal impairment. This should be considered when selecting the Bupivacaine Hydrochloride Injection/Bupivacaine Hydrochloride and Epinephrine Injection dosage [see Use in Specific Populations (8.5)] .

10 OVERDOSAGE

Clinical Presentation

Acute emergencies from use of Bupivacaine Hydrochloride Injection/Bupivacaine Hydrochloride and Epinephrine Injection are generally related to high plasma levels encountered during therapeutic use or to unintended intrathecal injection [see Warnings and Precautions (5.2, 5.9), Adverse Reactions (6)].

If not treated immediately, convulsions with simultaneous hypoxia, hypercarbia, and acidosis plus myocardial depression from the direct effects of bupivacaine may result in cardiac arrhythmias, bradycardia, asystole, ventricular fibrillation, or cardiac arrest. Respiratory abnormalities, including apnea, may occur. Hypoventilation or apnea due to unintentional intrathecal injection of Bupivacaine Hydrochloride Injection/Bupivacaine Hydrochloride and Epinephrine Injection may produce these same signs and also lead to cardiac arrest if ventilatory support is not instituted. If cardiac arrest should occur, successful outcome may require prolonged resuscitative efforts.

Management

The first step in the management of systemic toxic reactions, as well as hypoventilation or apnea due to unintentional intrathecal injection of Bupivacaine Hydrochloride Injection/Bupivacaine Hydrochloride and Epinephrine Injection, consists of immediateattention to the establishment and maintenance of a patent airway and effective assisted or controlled ventilation with 100% oxygen with a delivery system capable of permitting immediate positive airway pressure by mask. Endotracheal intubation, using drugs and techniques familiar to the clinician, may be indicated after initial administration of oxygen by mask if difficulty is encountered in the maintenance of a patent airway, or if prolonged ventilatory support (assisted or controlled) is indicated.

If necessary, use drugs to manage the convulsions. A bolus intravenous dose of a benzodiazepine will counteract CNS stimulation related to Bupivacaine Hydrochloride Injection. Immediately after the institution of ventilatory measures, evaluate the adequacy of the circulation. Supportive treatment of circulatory depression may require Advance Cardiac Life Support measures.

11 DESCRIPTION

Bupivacaine Hydrochloride Injection contains bupivacaine hydrochloride, an amide local anesthetic, as the active pharmaceutical ingredient. The route of administration for Bupivacaine Hydrochloride Injection (without epinephrine) is by injection, for infiltration, perineural, caudal, epidural, or retrobulbar use. Multiple-dose vials contain methylparaben [see Warnings and Precautions (5.4)] .

Bupivacaine hydrochloride is 2-piperidinecarboxamide, 1-butyl- N-(2,6-dimethylphenyl)-, monohydrochloride, monohydrate. It is a white crystalline powder that is freely soluble in 95 percent ethanol, soluble in water, and slightly soluble in chloroform or acetone. It has the following structural formula:

Bupivacaine Hydrochloride Injection, USP is a clear and colorless sterile isotonic solution. Each mL of single-dose vial contains 2.5 mg, 5 mg, or 7.5 mg of bupivacaine hydrochloride (equivalent to 2.22 mg, 4.44 mg, or 6.66 mg of bupivacaine, respectively), sodium chloride for isotonicity, sodium hydroxide or hydrochloric acid to adjust the pH between 4 and 6.5, in water for injection.

For the multiple-dose vials, each mL also contains 1 mg methylparaben as preservative.

12 CLINICAL PHARMACOLOGY

12.1 Mechanism of Action

Bupivacaine blocks the generation and the conduction of nerve impulses, presumably by increasing the threshold for electrical excitation in the nerve, by slowing the propagation of the nerve impulse, and by reducing the rate of rise of the action potential. In general, the progression of anesthesia is related to the diameter, myelination, and conduction velocity of affected nerve fibers. Clinically, the order of loss of nerve function is as follows: (1) pain, (2) temperature, (3) touch, (4) proprioception, and (5) skeletal muscle tone.

Epinephrine is a vasoconstrictor added to bupivacaine to slow absorption into the general circulation and thus prolong maintenance of an active tissue concentration.

12.2 Pharmacodynamics

Systemic absorption of bupivacaine produces effects on the cardiovascular system and CNS. At blood concentrations achieved with normal therapeutic doses, changes in cardiac conduction, excitability, refractoriness, contractility, and peripheral vascular resistance are minimal. However, toxic blood concentrations depress cardiac conduction and excitability, which may lead to atrioventricular block, ventricular arrhythmias, and cardiac arrest, sometimes resulting in fatalities. In addition, myocardial contractility is depressed and peripheral vasodilation occurs, leading to decreased cardiac output and arterial blood pressure. These cardiovascular changes are more likely to occur after unintended intravascular injection of bupivacaine [see Warnings and Precautions (5.9)] .

Following systemic absorption, bupivacaine can produce CNS stimulation, CNS depression, or both. Apparent central stimulation is manifested as restlessness, tremors, and shivering, progressing to convulsions, followed by CNS depression and coma progressing ultimately to respiratory arrest. However, bupivacaine has a primary depressant effect on the medulla and on higher centers. The depressed stage may occur without a prior excited state.

The duration of local anesthesia after administration of Bupivacaine Hydrochloride Injection is longer than that observed after administration of other commonly used short-acting local anesthetics. There appears to be period of analgesia that persists after the resolution of the block and return of sensation.

The onset of action following dental injections is usually 2 to 10 minutes and may last up to 7 hours. The duration of anesthetic effect is prolonged by the addition of epinephrine 1:200,000.

12.3 Pharmacokinetics

Systemic plasma levels of bupivacaine following administration of Bupivacaine Hydrochloride Injection do not correlate with local efficacy.

Absorption

The rate of systemic absorption of bupivacaine is dependent upon the total dose and concentration of drug administered, the route of administration, the vascularity of the administration site, and the presence or absence of epinephrine in the anesthetic solution. A dilute concentration of epinephrine (1:200,000) usually reduces the rate of absorption and peak plasma concentration of bupivacaine, permitting the use of moderately larger total doses and sometimes prolonging the duration of action [see Dosage and Administration (2)] .

After injection of Bupivacaine Hydrochloride Injection for caudal, epidural, or peripheral nerve block, peak levels of bupivacaine in the blood are reached in 30 to 45 minutes, followed by a decline to insignificant levels during the next three to six hours.

Distribution

Bupivacaine appears to cross the placenta by passive diffusion. The rate and degree of diffusion is governed by (1) the degree of plasma protein binding, (2) the degree of ionization, and (3) the degree of lipid solubility. Fetal/maternal ratios of bupivacaine appear to be inversely related to the degree of plasma protein binding, because only the free, unbound drug is available for placental transfer. Bupivacaine with a high protein binding capacity (95%) has a low fetal/maternal ratio (0.2 to 0.4). The extent of placental transfer is also determined by the degree of ionization and lipid solubility of the drug. Lipid soluble, nonionized drugs readily enter the fetal blood from the maternal circulation.

Depending upon the route of administration, bupivacaine is distributed to some extent to all body tissues, with high concentrations found in highly perfused organs such as the liver, lungs, heart, and brain.

Pharmacokinetic studies on the plasma profile of bupivacaine after direct intravenous injection (Bupivacaine Hydrochloride Injection is not approved for intravenous use) suggest a three-compartment open model. The first compartment is represented by the rapid intravascular distribution of the drug. The second compartment represents the equilibration of the drug throughout the highly perfused organs such as the brain, myocardium, lungs, kidneys, and liver. The third compartment represents an equilibration of the drug with poorly perfused tissues, such as muscle and fat.

Elimination

The half-life of bupivacaine in adults is 2.7 hours.

Metabolism

Amide-type local anesthetics such as bupivacaine are metabolized primarily in the liver via conjugation with glucuronic acid. Pipecoloxylidine is the major metabolite of bupivacaine. The elimination of drug from tissue distribution depends largely upon the availability of binding sites in the circulation to carry it to the liver where it is metabolized.

Excretion

The kidney is the main excretory organ for most local anesthetics and their metabolites. Urinary excretion is affected by urinary perfusion and factors affecting urinary pH. Only 6% of bupivacaine is excreted unchanged in the urine.

Specific Populations

Geriatric Patients

Elderly patients exhibited higher peak plasma concentrations than younger patients following administration of Bupivacaine Hydrochloride Injection. The total plasma clearance was decreased in these patients [see Use in Specific Populations (8.5)] .

Patients with Hepatic Impairment

Various pharmacokinetic parameters of the local anesthetics can be significantly altered by the presence of hepatic disease. Patients with hepatic disease, especially those with severe hepatic disease, may be more susceptible to the potential toxicities of the amide-type local anesthetics [see Use in Specific Populations (8.6)] .

Patients with Renal Impairment

Various pharmacokinetic parameters of the local anesthetics can be significantly altered by the presence of renal disease, factors affecting urinary pH, and renal blood flow [see Use in Specific Populations (8.5, 8.7)] .

13 NONCLINICAL TOXICOLOGY

13.1 Carcinogenesis, Mutagenesis, Impairment of Fertility

Carcinogenesis

Long-term studies in animals to evaluate the carcinogenic potential of bupivacaine hydrochloride have not been conducted.

Mutagenesis

The mutagenic potential of bupivacaine hydrochloride has not been determined.

Impairment of Fertility

The effect of bupivacaine on fertility has not been determined.

16 HOW SUPPLIED/STORAGE AND HANDLING

STORAGE AND HANDLING

Store at 20 °C to 25 °C (68 °F to 77 °F); excursions permitted between 15 °C to 30 °C (59 °F to 86 °F). [See USP Controlled Room Temperature.]

Bupivacaine Hydrochloride Injection, USP─ Solutions of bupivacaine hydrochloride that do not contain epinephrine may be autoclaved. Autoclave at 15-pound pressure, 121 °C (250 °F) for 15 minutes. This product is clear and colorless. Do not use the solution if it is discolored or if it contains a precipitate.

Unit of Sale | Concentration
NDC 0409-1159-01 Tray of 25 single-dose teartop vials | 0.25% 25 mg/10 mL (2.5 mg/mL)
NDC 0409-1159-02 Tray of 25 single-dose teartop vials | 0.25% 75 mg/30 mL (2.5 mg/mL)
NDC 0409-1160-01 Tray of 25 multiple-dose fliptop vials | 0.25% 125 mg/50 mL (2.5 mg/mL)
NDC 0409-1163-01 Tray of 25 multiple-dose fliptop vials | 0.5% 250 mg/50 mL (5 mg/mL)
NDC 0409-1162-01 Tray of 25 single-dose teartop vials | 0.5% 50 mg/10 mL (5 mg/mL)
NDC 0409-1162-02 Tray of 25 single-dose teartop vials | 0.5% 150 mg/30 mL (5 mg/mL)
NDC 0409-1165-01 Tray of 25 single-dose teartop vials | 0.75% 75 mg/10 mL (7.5 mg/mL)
NDC 0409-1165-02 Tray of 25 single-dose teartop vials | 0.75% 225 mg/30 mL (7.5 mg/mL)

For single-dose vials: Discard unused portion.

17 PATIENT COUNSELING INFORMATION

Allergic-Type Reactions

Assess if the patient has had allergic-type reactions to amide-type local anesthetics or to other formulation ingredients, such as the antimicrobial preservative methylparaben contained in multiple-dose vials or sulfites in epinephrine-containing solutions [see Contraindications (4), Warnings and Precautions (5.8), Adverse Reactions (6)].

Temporary Loss of Sensation and Motor Activity After Caudal or Epidural Anesthesia

When appropriate, patients should be informed in advance that they may experience temporary loss of sensation and motor activity, usually in the lower half of the body, following proper administration of caudal or epidural anesthesia.

Instructions After Dental Injection of Bupivacaine Hydrochloride Injection

Advise patients receiving dental injections of Bupivacaine Hydrochloride Injection not to chew solid foods or to test the anesthetized area by biting or probing until anesthesia has worn off (up to 7 hours) [see Warnings and Precautions (5.16)].

Methemoglobinemia

Inform patients that use of local anesthetics may cause methemoglobinemia, a serious condition that must be treated promptly. Advise patients or caregivers to seek immediate medical attention if they or someone in their care experience the following signs or symptoms: pale, gray, or blue colored skin (cyanosis); headache; rapid heart rate; shortness of breath; lightheadedness; or fatigue [see Warnings and Precautions (5.3)].

This product's labeling may have been updated. For the most recent prescribing information, please visit www.pfizer.com.

Distributed by Hospira, Inc., Lake Forest, IL 60045 USA

LAB-1176-5.0

Methylprednisolone Acetate Injectable Suspension, USP
80 mg/mL (1 mL)
Rx only
Single-Dose Vial
Not For Intravenous Use

DESCRIPTION

Methylprednisolone acetate injectable suspension, USP is an anti-inflammatory glucocorticoid for intramuscular, intra-articular, soft tissue or intralesional injection. It is available as single-dose vials in 80 mg/mL strength

Each mL of these preparations contains:

## | 80 mg/mL
Methylprednisolone Acetate, USP | 80 mg
Polyethylene glycol 3350 | 28 mg
Myristyl-gamma-picolinium chloride | 0.189 mg

Sodium chloride was added to adjust tonicity.

When necessary, pH was adjusted with sodium hydroxide and/or hydrochloric acid.

The pH of the finished product remains within the USP specified range (e.g., 3.0 to 7.0).

The chemical name for methylprednisolone acetate is pregna-1,4-diene-3,20-dione, 21-(acetyloxy)-11,17-dihydroxy-6-methyl-,(6α,11β)- and the molecular weight is 416.51. The structural formula is represented below:

Methylprednisolone acetate injectable suspension, USP contains methylprednisolone acetate, USP which is the 6-methyl derivative of prednisolone. Methylprednisolone acetate, USP is a white or almost white crystalline powder which melts at about 213° with some decomposition. It is soluble in dioxane, sparingly soluble in acetone, alcohol, chloroform, and methanol, and slightly soluble in ether. It is practically insoluble in water.

CLINICAL PHARMACOLOGY

Glucocorticoids, naturally occurring and synthetic, are adrenocortical steroids.

Naturally occurring glucocorticoids (hydrocortisone and cortisone), which also have salt retaining properties, are used in replacement therapy in adrenocortical deficiency states. Their synthetic analogs are used primarily for their anti-inflammatory effects in disorders of many organ systems.

INDICATIONS AND USAGE

A. For Intramuscular Administration

When oral therapy is not feasible and the strength, dosage form, and route of administration of the drug reasonably lend the preparation to the treatment of the condition, the intramuscular use of methylprednisolone acetate injectable suspension is indicated as follows:

Allergic States: Control of severe or incapacitating allergic conditions intractable to adequate trials of conventional treatment in asthma, atopic dermatitis, contact dermatitis, drug hypersensitivity reactions, serum sickness, transfusion reactions.

Dermatologic Diseases: Bullous dermatitis herpetiformis, exfoliative dermatitis, mycosis fungoides, pemphigus, severe erythema multiforme (Stevens-Johnson syndrome).

Endocrine Disorders: Primary or secondary adrenocortical insufficiency (hydrocortisone or cortisone is the drug of choice; synthetic analogs may be used in conjunction with mineralocorticoids where applicable; in infancy, mineralocorticoid supplementation is of particular importance), congenital adrenal hyperplasia, hypercalcemia associated with cancer, nonsupportive thyroiditis.

Gastrointestinal Diseases: To tide the patient over a critical period of the disease in regional enteritis (systemic therapy) and ulcerative colitis.

Hematologic Disorders: Acquired (autoimmune) hemolytic anemia, congenital (erythroid) hypoplastic anemia (Diamond Blackfan anemia), pure red cell aplasia, select cases of secondary thrombocytopenia.

Miscellaneous: Trichinosis with neurologic or myocardial involvement, tuberculous meningitis with subarachnoid block or impending block when used concurrently with appropriate antituberculous chemotherapy.

Neoplastic Diseases: For palliative management of: leukemias and lymphomas.

Nervous System: Cerebral edema associated with primary or metastatic brain tumor or craniotomy.

Ophthalmic Diseases: Sympathetic ophthalmia, temporal arteritis, uveitis, ocular inflammatory conditions unresponsive to topical corticosteroids.

Renal Diseases: To induce diuresis or remission of proteinuria in idiopathic nephrotic syndrome, or that due to lupus erythematosus.

Respiratory Diseases: Berylliosis, fulminating or disseminated pulmonary tuberculosis when used concurrently with appropriate antituberculous chemotherapy, idiopathic eosinophilic pneumonias, symptomatic sarcoidosis.

Rheumatic Disorders: As adjunctive therapy for short-term administration (to tide the patient over an acute episode or exacerbation) in acute gouty arthritis; acute rheumatic carditis; ankylosing spondylitis; psoriatic arthritis; rheumatoid arthritis, including juvenile rheumatoid arthritis (selected cases may require low-dose maintenance therapy). For the treatment of dermatomyositis, polymyositis, and systemic lupus erythematosus.

B. For Intra-articular Or Soft Tissue Administration

(See WARNINGS)

Methylprednisolone acetate injectable suspension is indicated as adjunctive therapy for short-term administration (to tide the patient over an acute episode or exacerbation) in acute gouty arthritis, acute and subacute bursitis, acute nonspecific tenosynovitis, epicondylitis, rheumatoid arthritis, synovitis of osteoarthritis.

C. For Intralesional Administration

Methylprednisolone acetate injectable suspension is indicated for intralesional use in alopecia areata, discoid lupus erythematosus; keloids, localized hypertrophic, infiltrated inflammatory lesions of granuloma annulare, lichen planus, lichen simplex chronicus (neurodermatitis) and psoriatic plaques; necrobiosis lipoidica diabeticorum.

Methylprednisolone acetate injectable suspension also may be useful in cystic tumors of an aponeurosis or tendon (ganglia).

CONTRAINDICATIONS

Methylprednisolone acetate injectable suspension is contraindicated in patients with known hypersensitivity to the product and its constituents.

Intramuscular corticosteroid preparations are contraindicated for idiopathic thrombocytopenic purpura.
Methylprednisolone acetate injectable suspension is contraindicated for intrathecal administration. This formulation of methylprednisolone acetate has been associated with reports of severe medical events when administered by this route.

Methylprednisolone acetate injectable suspension is contraindicated in systemic fungal infections, except when administered as an intra-articular injection for localized joint conditions (see WARNINGS: Infections, Fungal Infections).

WARNINGS

Serious Neurologic Adverse Reactions with Epidural Administration

Serious neurologic events, some resulting in death, have been reported with epidural injection of corticosteroids. Specific events reported include, but are not limited to, spinal cord infarction, paraplegia, quadriplegia, cortical blindness, and stroke. These serious neurologic events have been reported with and without use of fluoroscopy. The safety and effectiveness of epidural administration of corticosteroids have not been established, and corticosteroids are not approved for this use.

General

This product is not suitable for multi-dose use. Following administration of the desired dose, any remaining suspension should be discarded.

Injection of methylprednisolone acetate may result in dermal and/or subdermal changes forming depressions in the skin at the injection site.

In order to minimize the incidence of dermal and subdermal atrophy, care must be exercised not to exceed recommended doses in injections. Multiple small injections into the area of the lesion should be made whenever possible. The technique of intra-articular and intramuscular injection should include precautions against injection or leakage into the dermis. Injection into the deltoid muscle should be avoided because of a high incidence of subcutaneous atrophy.

It is critical that, during administration of methylprednisolone acetate injectable suspension, appropriate technique be used and care taken to ensure proper placement of drug.

Rare instances of anaphylactoid reactions have occurred in patients receiving corticosteroid therapy (see ADVERSE REACTIONS).

Increased dosage of rapidly acting corticosteroids is indicated in patients on corticosteroid therapy subjected to any unusual stress before, during, and after the stressful situation.

Results from one multicenter, randomized, placebo-controlled study with methylprednisolone hemisuccinate, an IV corticosteroid, showed an increase in early (at 2 weeks) and late (at 6 months) mortality in patients with cranial trauma who were determined not to have other clear indications for corticosteroid treatment. High doses of systemic corticosteroids, including methylprednisolone acetate, should not be used for the treatment of traumatic brain injury.

Cardio-renal

Average and large doses of corticosteroids can cause elevation of blood pressure, salt and water retention, and increased excretion of potassium. These effects are less likely to occur with synthetic derivatives when used in large doses. Dietary salt restriction and potassium supplementation may be necessary. All corticosteroids increase calcium excretion.

Literature reports suggest an apparent association between use of corticosteroids and left ventricular free wall rupture after a recent myocardial infarction; therefore, therapy with corticosteroids should be used with great caution in these patients.

Endocrine

Hypothalamic-pituitary adrenal (HPA) axis suppression. Cushing’s syndrome, and Hyperglycemia: Monitor patients for these conditions with chronic use.

Corticosteroids can produce reversible HPA axis suppression with the potential for glucocorticosteroid insufficiency after withdrawal of treatment. Drug induced secondary adrenocortical insufficiency may be minimized by gradual reduction of dosage. This type of relative insufficiency may persist for months after discontinuation of therapy; therefore, in any situation of stress occurring during that period, hormone therapy should be reinstituted.

Infections

General

Persons who are on corticosteroids are more susceptible to infections than are healthy individuals. There may be decreased resistance and inability to localize infection when corticosteroids are used. Infections with any pathogen (viral, bacterial, fungal, protozoan, or helminthic) in any location of the body, may be associated with the use of corticosteroids alone or in combination with other immunosuppressive agents.

These infections may be mild, but can be severe and at times fatal. With increasing doses of corticosteroids, the rate of occurrence of infectious complications increases. Do not use intra-articularly, intrabursally, or for intratendinous administration for local effect in the presence of an acute infection. Corticosteroids may mask some signs of infection and new infections may appear during their use.

Fungal Infections

Corticosteroids may exacerbate systemic fungal infections and therefore should not be used in the presence of such infections unless they are needed to control drug interactions. There have been cases reported in which concomitant use of amphotericin B and hydrocortisone was followed by cardiac enlargement and congestive heart failure (see CONTRAINDICATIONSand PRECAUTIONS: Drug Interactions, Amphotericin B injection and potassium-depleting agents).

Special Pathogens

Latent disease may be activated or there may be an exacerbation of intercurrent infections due to pathogens, including those caused by Amoeba, Candida, Cryptococcus, Mycobacterium, Nocardia, Pneumocystis,and Toxoplasma.

It is recommended that latent amebiasis or active amebiasis be ruled out before initiating corticosteroid therapy in any patient who has spent time in the tropics or in any patient with unexplained diarrhea.

Similarly, corticosteroids should be used with great care in patients with known or suspected Strongyloides(threadworm) infestation. In such patients, corticosteroid-induced immunosuppression may lead to Strongyloideshyperinfection and dissemination with widespread larval migration, often accompanied by severe enterocolitis and potentially fatal gram-negative septicemia.

Corticosteroids should not be used in cerebral malaria. There is currently no evidence of benefit from steroids in this condition.

Tuberculosis

The use of corticosteroids in active tuberculosis should be restricted to those cases of fulminating or disseminated tuberculosis in which the corticosteroid is used for the management of the disease in conjunction with an appropriate antituberculous regimen.

If corticosteroids are indicated in patients with latent tuberculosis or tuberculin reactivity, close observation is necessary, as reactivation of the disease may occur. During prolonged corticosteroid therapy, these patients should receive chemoprophylaxis.

Vaccinations

Administration of live or live, attenuated vaccines is contraindicated in patients receiving immunosuppressive doses of corticosteroids. Killed or inactivated vaccines may be administered. However, the response to such vaccines cannot be predicted.

Immunization procedures may be undertaken in patients who are receiving corticosteroids as replacement therapy (e.g., for Addison’s disease).

Viral Infections

Chicken pox and measles can have a more serious or even fatal course in pediatric and adult patients on corticosteroids. In pediatric and adult patients who have not had these diseases, particular care should be taken to avoid exposure. The contribution of the underlying disease and/or prior corticosteroid treatment to the risk is also not known. If exposed to chicken pox, prophylaxis with varicella zoster immune globulin (VZIG) may be indicated. If exposed to measles, prophylaxis with immunoglobulin (IG) may be indicated (see the respective package inserts for complete VZIG and IG prescribing information). If chicken pox develops, treatment with antiviral agents should be considered.

Ophthalmic

Use of corticosteroids may produce posterior subcapsular cataracts, glaucoma with possible damage to the optic nerves, and may enhance the establishment of secondary ocular infections due to bacteria, fungi, or viruses. The use of systemic corticosteroids is not recommended in the treatment of optic neuritis and may lead to an increase in the risk of new episodes. Corticosteroids should be used cautiously in patients with ocular herpes simplex because of corneal perforation. Corticosteroids should not be used in active ocular herpes simplex.

PRECAUTIONS

General

This product, like many other corticosteroids, is sensitive to heat. Therefore, it should not be autoclaved when it is desirable to sterilize the exterior of the vial.

The lowest possible dose of corticosteroid should be used to control the condition under treatment. When reduction in dosage is possible, the reduction should be gradual.

Since complications of treatment with glucocorticosteroids are dependent on the size of the dose and the duration of treatment, a risk/benefit decision must be made in each individual case as to dose and duration of treatment and as to whether daily or intermittent therapy should be used.

Karposi’s sarcoma has been reported to occur in patients receiving corticosteroid therapy, most often for chronic conditions. Discontinuation of corticosteroids may result in clinical improvement.

Cardio-renal

Caution is required in patients with systemic sclerosis because an increased incidence of scleroderma renal crisis has been observed with corticosteroids, including methylprednisolone.

As sodium retention with resultant edema and potassium loss may occur in patients receiving corticosteroids, these agents should be used with caution in patients with congestive heart failure or renal insufficiency.

Endocrine

Drug-induced secondary adrenocortical insufficiency may be minimized by gradual reduction of dosage. This type of relative insufficiency may persist for months after discontinuation of therapy; therefore, in any situation of stress occurring during that period, hormone therapy should be reinstituted.

Metabolic clearance of corticosteroids is decreased in hypothyroid patients and increased in hyperthyroid patients. Changes in thyroid status of the patient may necessitate adjustment in dosage.

Gastrointestinal

Steroids should be used with caution in active or latent peptic ulcers, diverticulitis, fresh intestinal anastomoses, and nonspecific ulcerative colitis, since they may increase the risk of perforation.

Signs of peritoneal irritation following gastrointestinal perforation in patients receiving corticosteroids may be minimal or absent.

There is an enhanced effect due to decreased metabolism of corticosteroids in patients with cirrhosis.

Parenteral Administration

Intra-articularly injected corticosteroids may be systemically absorbed.

Appropriate examination of any joint fluid present is necessary to exclude a septic process.

A marked increase in pain accompanied by local swelling, further restriction of joint motion, fever, and malaise are suggestive of septic arthritis. If this complication occurs and diagnosis of sepsis is confirmed, appropriate antimicrobial therapy should be instituted.

Injection of a steroid into an infected site is to be avoided. Local injection of a steroid into a previously infected joint is not usually recommended.

Musculoskeletal

Corticosteroids decrease bone formation and increase bone resorption both through their effect on calcium regulation (e.g., decreasing absorption and increasing excretion) and inhibition of osteoblast function. This, together with a decrease in the protein matrix of the bone secondary to an increase in protein catabolism, and reduced sex hormone production, may lead to an inhibition of bone growth in pediatric patients and the development of osteoporosis at any age. Special consideration should be given to patients at increased risk of osteoporosis (i.e. postmenopausal women) before initiating corticosteroid therapy.

Neuro-psychiatric

An acute myopathy has been observed with the use of high doses of corticosteroids, most often occurring in patients with disorders of neuromuscular transmission (e.g., myasthenia gravis), or in patients receiving concomitant therapy with neuromuscular blocking drugs (e.g., pancuronium). This acute myopathy is generalized, may involve ocular and respiratory muscles, and may result in quadriparesis. Elevation of creatine kinase may occur. Clinical improvement or recovery after stopping corticosteroids may require weeks to years.

Psychic derangements may appear when corticosteroids are used, ranging from euphoria, insomnia, mood swings, personality changes, and severe depression to frank psychotic manifestations. Also, existing emotional instability or psychotic tendencies may be aggravated by corticosteroids.

Ophthalmic

Intraocular pressure may become elevated in some individuals. If steroid therapy is continued long-term, intraocular pressure should be monitored.

Corticosteroids should be used cautiously in patients with ocular herpes simplex for fear of corneal perforation.

Information for the Patient

Patients should be warned not to discontinue the use of corticosteroids abruptly or without medical supervision, to advise any medical attendants that they are taking corticosteroids and to seek medical advice at once should they develop a fever or other signs of infection.

Persons who are on corticosteroids should be warned to avoid exposure to chicken pox or measles. Patients should also be advised that if they are exposed, medical advice should be sought without delay.

Drug Interactions

Aminoglutethimide: Aminoglutethimide may lead to a loss of corticosteroid-induced adrenal suppression.

Amphotericin B injection and potassium-depleting agents:When corticosteroids are administered concomitantly with potassium depleting agents (e.g., amphotericin B, diuretics), patients should be observed closely for development of hypokalemia. There have been cases reported in which concomitant use of amphotericin B and hydrocortisone was followed by cardiac enlargement and congestive heart failure.

Antibiotics: Macrolide antibiotics have been reported to cause a significant decrease in corticosteroid clearance (see PRECAUTIONS: Drug Interactions, Hepatic Enzyme Inhibitors).

Anticholinesterases:Concomitant use of anticholinesterase agents and corticosteroids may produce severe weakness in patients with myasthenia gravis. If possible, anticholinesterase agents should be withdrawn at least 24 hours before initiating corticosteroid therapy.

Anticoagulants, oral: Co-administration of corticosteroids and warfarin usually results in inhibition of response to warfarin, although there have been some conflicting reports. Therefore, coagulation indices should be monitored frequently to maintain the desired anticoagulant effect.

Antidiabetics:Because corticosteroids may increase blood glucose concentration, dosage adjustments of antidiabetic agents may be required.

Antitubercular drugs:Serum concentrations of isoniazid may be decreased.

Cholestyramine:Cholestyramine may increase the clearance of oral corticosteroids.

Cyclosporine:Increased activity of both cyclosporine and corticosteroids may occur when the two are used concurrently. Convulsions have been reported with this concurrent use.

Digitalis glycosides:Patients on digitalis glycosides may be at risk of arrhythmias due to hypokalemia.

Estrogens, including oral contraceptives:Estrogens may decrease the hepatic metabolism of certain corticosteroids, thereby increasing their effect.

Hepatic Enzyme Inducers (e.g., barbiturates, phenytoin, carbamazepine, rifampin):Drugs which induce cytochrome P450 3A4 enzyme activity may enhance the metabolism of corticosteroids and require that the dosage of the corticosteroid be increased.

Hepatic Enzyme Inhibitors (e.g., ketoconazole, macrolide antibiotics such as erythromycin and troleandomycin):Drugs which inhibit cytochrome P450 3A4 have the potential to result in increased plasma concentrations of corticosteroids.

Ketoconazole: Ketoconazole has been reported to significantly decrease the metabolism of certain corticosteroids by up to 60%, leading to an increased risk of corticosteroid side effects.

Nonsteroidal anti-inflammatory drugs (NSAIDs): Concomitant use of aspirin (or other nonsteroidal anti-inflammatory agents) and corticosteroids increases the risk of gastrointestinal side effects. Aspirin should be used cautiously in conjunction with corticosteroids in hypoprothrombinemia. The clearance of salicylates may be increased with concurrent use of corticosteroids.

Skin tests: Corticosteroids may suppress reactions to skin tests.

Vaccines: Patients on prolonged corticosteroid therapy may exhibit a diminished response to toxoids and live or inactivated vaccines due to inhibition of antibody response. Corticosteroids may also potentiate the replication of some organisms contained in live attenuated vaccines. Routine administration of vaccines or toxoids should be deferred until corticosteroid therapy is discontinued if possible (see WARNINGS: Infections, Vaccinations).

Carcinogenesis, Mutagenesis, Impairment of Fertility

No adequate studies have been conducted in animals to determine whether corticosteroids have a potential for carcinogenesis or mutagenesis.

Steroids may increase or decrease motility and number of spermatozoa in some patients.

Corticosteroids have been shown to impair fertility in male rats.

Pregnancy: Teratogenic Effects

Corticosteroids have been shown to be teratogenic in many species when given in doses equivalent to the human dose. Animal studies in which corticosteroids have been given to pregnant mice, rats, and rabbits have yielded an increased incidence of cleft palate in the offspring. There are no adequate and well-controlled studies in pregnant women. Corticosteroids should be used during pregnancy only if the potential benefit justifies the potential risk to the fetus. Infants born to mothers who have received corticosteroids during pregnancy should be carefully observed for signs of hypoadrenalism.

Nursing Mothers

Systemically administered corticosteroids appear in human milk and could suppress growth, interfere with endogenous corticosteroid production, or cause other untoward effects. Because of the potential for serious adverse reactions in nursing infants from corticosteroids, a decision should be made whether to discontinue nursing or discontinue the drug, taking into account the importance of the drug to the mother.

Pediatric Use

The efficacy and safety of corticosteroids in the pediatric population are based on the well-established course of effect of corticosteroids which is similar in pediatric and adult populations. Published studies provide evidence of efficacy and safety in pediatric patients for the treatment of nephritic syndrome (patients > 2 years of age) and aggressive lymphomas and leukemias (patients > 1 month of age). Other indications for pediatric use of corticosteroids (e.g., severe asthma and wheezing) are based on adequate and well-controlled clinical trials conducted in adults, on the premises that the course of the diseases and their pathophysiology are considered to be substantially similar in both populations.

The adverse effects of corticosteroids in pediatric patients are similar to those in adults (see ADVERSE REACTIONS). Like adults, pediatric patients should be carefully observed with frequent measurements of blood pressure, weight, height, intraocular pressure, and clinical evaluation for the presence of infection, psychosocial disturbances, thromboembolism, peptic ulcers, cataracts, and osteoporosis. Pediatric patients who are treated with corticosteroids by any route, including systemically administered corticosteroids, may experience a decrease in their growth velocity. This negative impact of corticosteroids on growth has been observed at low systemic doses and in the absence of laboratory evidence of HPA axis suppression (i.e. cosyntropin stimulation and basal cortisol plasma levels). Growth velocity may therefore be a more sensitive indicator of systemic corticosteroid exposure in pediatric patients than some commonly used tests of HPA axis function. The linear growth of pediatric patients treated with corticosteroids should be monitored, and the potential growth effects of prolonged treatment should be weighed against clinical benefits obtained and the availability of treatment alternatives. In order to minimize the potential growth effects of corticosteroids, pediatric patients should be titrated to the lowest effective dose.

Geriatric Use

Clinical studies did not include sufficient numbers of subjects aged 65 and over to determine whether they respond differently from younger subjects. Other reported clinical experience has not identified differences in responses between the elderly and younger patients. In general, dose selection for an elderly patient should be cautious, usually starting at the low end of the dosing range, reflecting the greater frequency of decreased hepatic, renal, or cardiac function, and of concomitant disease or other drug therapy.

ADVERSE REACTIONS

The following adverse reactions have been reported with methylprednisolone acetate or other corticosteroids:

Allergic reactions:Allergic or hypersensitivity reactions, anaphylactoid reaction, anaphylaxis, angioedema.

Blood and lymphatic system disorders:Leukocytosis.

Cardiovascular:Bradycardia, cardiac arrest, cardiac arrhythmias, cardiac enlargement, circulatory collapse, congestive heart failure, fat embolism, hypertension, hypertrophic cardiomyopathy in premature infants, myocardial rupture following recent myocardial infarction (see WARNINGS), pulmonary edema, syncope, tachycardia, thromboembolism, thrombophlebitis, vasculitis.

Dermatologic:Acne, allergic dermatitis, cutaneous and subcutaneous atrophy, dry scaly skin, ecchymoses and petechiae, edema, erythema, hyperpigmentation, hypopigmentation, impaired wound healing, increased sweating, rash, sterile abscess, striae, suppressed reactions to skin tests, thin fragile skin, thinning scalp hair, urticaria.

Endocrine:Decreased carbohydrate and glucose tolerance, development of cushingoid state, glycosuria, hirsutism, hypertrichosis, increased requirements for insulin or oral hypoglycemic agents in diabetes, manifestations of latent diabetes mellitus, menstrual irregularities, secondary adrenocortical and pituitary unresponsiveness (particularly in times of stress, as in trauma, surgery, or illness), suppression of growth in pediatric patients.

Fluid and electrolyte disturbances: Congestive heart failure in susceptible patients, fluid retention, hypokalemic alkalosis, potassium loss, sodium retention.

Gastrointestinal: Abdominal distention, bowel/bladder dysfunction (after intrathecal administration), elevation in serum liver enzyme levels (usually reversible upon discontinuation), hepatomegaly, increased appetite, nausea, pancreatitis, peptic ulcer with possible subsequent perforation and hemorrhage, perforation of the small and large intestine (particularly in patients with inflammatory bowel disease), ulcerative esophagitis.

Metabolic: Negative nitrogen balance due to protein catabolism.

Musculoskeletal: Aseptic necrosis of femoral and humeral heads, calcinosis (following intra-articular or intra-lesional use), Charcot-like arthropathy, loss of muscle mass, muscle weakness, osteoporosis, pathologic fracture of long bones, postinjection flare (following intra-articular use), steroid myopathy, tendon rupture, vertebral compression fractures.

Neurologic/Psychiatric: Convulsions, depression, emotional instability, euphoria, headache, increased intracranial pressure with papilledema (pseudotumor cerebri) usually following discontinuation of treatment, insomnia, mood swings, neuritis, neuropathy, paresthesia, personality changes, psychic disorders, vertigo.

Ophthalmic: Exophthalmoses, glaucoma, increased intraocular pressure, posterior subcapsular cataracts.

Other:Abnormal fat deposits, decreased resistance to infection, hiccups, increased or decreased motility and number of spermatozoa, injection site infections following non-sterile administration (see WARNINGS), malaise, moon face, weight gain.

The following adverse reactions have been reported with the following routes of administration:

Intrathecal/Epidural: Arachnoiditis, bowel/bladder dysfunction, headache, meningitis, parapareisis/paraplegia, seizures, sensory disturbances.

Intranasal: Allergic reactions, rhinitis, temporary/permanent visual impairment including blindness.

Ophthalmic: Increased intraocular pressure, infection, ocular and periocular inflammation including allergic reactions, residue or slough at injection site, temporary/permanent visual impairment including blindness.

Miscellaneous injection sites(scalp, tonsillar fauces, sphenopalatine ganglion): Blindness.

To report SUSPECTED ADVERSE REACTIONS, contact Amneal Pharmaceuticals at 1-877-835-5472 or FDA at 1-800-FDA-1088 or www.fda.gov/medwatch.

OVERDOSAGE

Treatment of acute overdosage is by supportive and symptomatic therapy. For chronic overdosage in the face of severe disease requiring continuous steroid therapy, the dosage of the corticosteroid may be reduced only temporarily, or alternate day treatment may be introduced.

DOSAGE AND ADMINISTRATION

Because of possible physical incompatibilities, methylprednisolone acetate injectable suspension should not be diluted or mixed with other solutions.

The initial dosage of parenterally administered methylprednisolone acetate injectable suspension will vary from 4 mg to 120 mg, depending on the specific disease entity being treated. However, in certain overwhelming, acute, life-threatening situations, administration in dosages exceeding the usual dosages may be justified and may be in multiples of the oral dosages.

It Should Be Emphasized that Dosage Requirements Are Variable and Must Be Individualized on the Basis of the Disease Under Treatment and the Response of the Patient.After a favorable response is noted, the proper maintenance dosage should be determined by decreasing the initial drug dosage in small decrements at appropriate time intervals until the lowest dosage which will maintain an adequate clinical response is reached. Situations which may make dosage adjustments necessary are changes in clinical status secondary to remissions or exacerbations in the disease process, the patient’s individual drug responsiveness, and the effect of patient exposure to stressful situations not directly related to the disease entity under treatment. In this latter situation, it may be necessary to increase the dosage of the corticosteroid for a period of time consistent with the patient’s condition. If after long-term therapy the drug is to be stopped, it is recommended that it be withdrawn gradually rather than abruptly.

A. Administration for Local Effect

Therapy with methylprednisolone acetate injectable suspension does not obviate the need for the conventional measures usually employed. Although this method of treatment will ameliorate symptoms, it is in no sense a cure and the hormone has no effect on the cause of the inflammation.

1. Rheumatoid Arthritis and Osteoarthritis.The dose for intra-articular administration depends upon the size of the joint and varies with the severity of the condition in the individual patient. In chronic cases, injections may be repeated at intervals ranging from one to five or more weeks, depending upon the degree of relief obtained from the initial injection. The doses in the following table are given as a general guide:

Size of; Joint | Examples | Range; of Dosage
Large | Knees; Ankles; Shoulders | 20 mg to 80 mg
Medium | Elbows; Wrists | 10 mg to 40 mg
Small | Metacarpophalangeal; Interphalangeal; Sternoclavicular; Acromioclavicular | 4 mg to 10 mg

Procedure:It is recommended that the anatomy of the joint involved be reviewed before attempting intra-articular injection. In order to obtain the full anti-inflammatory effect, it is important that the injection be made into the synovial space. Employing the same sterile technique as for a lumbar puncture, a sterile 20 to 24 gauge needle (on a dry syringe) is quickly inserted into the synovial cavity. Procaine infiltration is elective. The aspiration of only a few drops of joint fluid proves the joint space has been entered by the needle. The injection site for each joint is determined by that location where the synovial cavity is most superficial and most free of large vessels and nerves.With the needle in place, the aspirating syringe is removed and replaced by a second syringe containing the desired amount of methylprednisolone acetate injectable suspension. The plunger is then pulled outward slightly to aspirate synovial fluid and to make sure the needle is still in the synovial space. After injection, the joint is moved gently a few times to aid mixing of the synovial fluid and the suspension. The site is covered with a small sterile dressing.

Suitable sites for intra-articular injection are the knee, ankle, wrist, elbow, shoulder, phalangeal, and hip joints. Since difficulty is not infrequently encountered in entering the hip joint, precautions should be taken to avoid any large blood vessels in the area. Joints not suitable for injection are those that are anatomically inaccessible such as the spinal joints and those like the sacroiliac joints that are devoid of synovial space. Treatment failures are most frequently the result of failure to enter the joint space. Little or no benefit follows injection into surrounding tissue. If failures occur when injections into the synovial spaces are certain, as determined by aspiration of fluid, repeated injections are usually futile.

If a local anesthetic is used prior to injection of methylprednisolone acetate injectable suspension, the anesthetic package insert should be read carefully and all the precautions observed.

2. Bursitis. The area around the injection site is prepared in a sterile way and a wheal at the site made with 1 percent procaine hydrochloride solution. A 20 to 24 gauge needle attached to a dry syringe is inserted into the bursa and the fluid aspirated. The needle is left in place and the aspirating syringe changed for a small syringe containing the desired dose. After injection, the needle is withdrawn and a small dressing applied.

3. Miscellaneous: Ganglion, Tendinitis, Epicondylitis.In the treatment of conditions such as tendinitis or tenosynovitis, care should be taken following application of a suitable antiseptic to the overlying skin to inject the suspension into the tendon sheath rather than into the substance of the tendon. The tendon may be readily palpated when placed on a stretch. When treating conditions such as epicondylitis, the area of greatest tenderness should be outlined carefully and the suspension infiltrated into the area. For ganglia of the tendon sheaths, the suspension is injected directly into the cyst. In many cases, a single injection causes a marked decrease in the size of the cystic tumor and may effect disappearance. The usual sterile precautions should be observed, of course, with each injection.

The dose in the treatment of the various conditions of the tendinous or bursal structures listed above varies with the condition being treated and ranges from 4 mg to 30 mg. In recurrent or chronic conditions, repeated injections may be necessary.

4. Injections for Local Effect in Dermatologic Conditions. Following cleansing with an appropriate antiseptic such as 70% alcohol, 20 mg to 60 mg is injected into the lesion. It may be necessary to distribute doses ranging from 20 mg to 40 mg by repeated local injections in the case of large lesions. Care should be taken to avoid injection of sufficient material to cause blanching since this may be followed by a small slough. One to four injections are usually employed, the intervals between injections varying with the type of lesion being treated and the duration of improvement produced by the initial injection.

B. Administration for Systemic Effect

The intramuscular dosage will vary with the condition being treated. When employed as a temporary substitute for oral therapy, a single injection during each 24-hour period of a dose of the suspension equal to the total daily oral dose of methylprednisolone tablets, USP is usually sufficient. When a prolonged effect is desired, the weekly dose may be calculated by multiplying the daily oral dose by 7 and given as a single intramuscular injection.

In pediatric patients, the initial dose of methylprednisolone may vary depending on the specific disease entity being treated. Dosage must be individualized according to the severity of the disease and response of the patient. The recommended dosage may be reduced for pediatric patients, but dosage should be governed by the severity of the condition rather than by strict adherence to the ratio indicated by age or body weight.

In patients with the adrenogenital syndrome, a single intramuscular injection of 40 mg every two weeks may be adequate. For maintenance of patients with rheumatoid arthritis, the weekly intramuscular dose will vary from 40 mg to 120 mg. The usual dosage for patients with dermatologic lesionsbenefited by systemic corticoid therapy is 40 mg to 120 mg of methylprednisolone acetate administered intramuscularly at weekly intervals for one to four weeks. In acute severe dermatitis due to poison ivy, relief may result within 8 to 12 hours following intramuscular administration of a single-dose of 80 mg to 120 mg. In chronic contact dermatitis, repeated injections at 5 to 10 day intervals may be necessary. In seborrheic dermatitis, a weekly dose of 80 mg may be adequate to control the condition.

Following intramuscular administration of 80 mg to 120 mg to asthmatic patients, relief may result within 6 to 48 hours and persist for several days to two weeks.

If signs of stress are associated with the condition being treated, the dosage of the suspension should be increased. If a rapid hormonal effect of maximum intensity is required, the intravenous administration of highly soluble methylprednisolone sodium succinate is indicated.

For the purpose of comparison, the following is the equivalent milligram dose of the various glucocorticoids:

Cortisone, 25 | Triamcinolone, 4
Hydrocortisone, 20 | Paramethasone, 2
Prednisolone, 5 | Betamethasone, 0.75
Prednisone, 5 | Dexamethasone, 0.75
Methylprednisolone, 4

These dose relationships apply only to oral or intravenous administration of these compounds. When these substances or their derivatives are injected intramuscularly or into joint spaces, their relative properties may be greatly altered.

HOW SUPPLIED

Methylprednisolone Acetate Injectable Suspension, USP is supplied as a white to off-white homogenous suspension in single-dose vial available in the following strength and package size:

80 mg/mL (1 mL)

Single vial in a carton: NDC 70121-1574-1

Store at 20° to 25°C (68° to 77°F) [see USP Controlled Room Temperature].

This product’s label may have been updated. For current full prescribing information, please visit www.amneal.com.

Manufactured by:

Amneal Pharmaceuticals Pvt. Ltd.

Parenteral Unit

Ahmedabad 382213, INDIA

Distributed by:

Amneal Pharmaceuticals LLC

Bridgewater, NJ 08807

Rev. 07-2021-05

Distributed by:
Advanced Rx Pharmacy of Tennessee, LLC

Lidocaine HCl Injection, USP

For Infiltration and Nerve Block Including Caudal and Epidural Use.

Preservative-Free

Rx only

DESCRIPTION

Lidocaine hydrochloride injection, USP is sterile, nonpyrogenic, aqueous solution that contains a local anesthetic agent and is administered parenterally by injection. See INDICATIONS AND USAGEsection for specific uses.
Lidocaine hydrochloride injection, USP contains lidocaine hydrochloride, which is chemically designated as acetamide, 2-(diethylamino)-N-(2,6-dimethylphenyl)-, monohydrochloride and has the molecular weight 270.8. Lidocaine hydrochloride (C14H22N2O • HCl) has the following structural formula:

Lidocaine hydrochloride injection, USP is a sterile, nonpyrogenic, isotonic solution containing sodium chloride. The pH of the solution is adjusted to approximately 6.5 (5.0 to 7.0) with sodium hydroxide and/or hydrochloric acid.

CLINICAL PHARMACOLOGY

Mechanism of Action

Lidocaine hydrochloride stabilizes the neuronal membrane by inhibiting the ionic fluxes required for the initiation and conduction of impulses thereby effecting local anesthetic action.

Hemodynamics

Excessive blood levels may cause changes in cardiac output, total peripheral resistance, and mean arterial pressure. With central neural blockade these changes may be attributable to block of autonomic fibers, a direct depressant effect of the local anesthetic agent on various components of the cardiovascular system, and/or the beta-adrenergic receptor stimulating action of epinephrine when present. The net effect is normally a modest hypotension when the recommended dosages are not exceeded.

Pharmacokinetics and Metabolism

Information derived from diverse formulations, concentrations and usages reveals that lidocaine hydrochloride is completely absorbed following parenteral administration, its rate of absorption depending, for example, upon various factors such as the site of administration and the presence or absence of a vasoconstrictor agent. Except for intravascular administration, the highest blood levels are obtained following intercostal nerve block and the lowest after subcutaneous administration.
The plasma binding of lidocaine hydrochloride is dependent on drug concentration, and the fraction bound decreases with increasing concentration. At concentrations of 1 to 4 mcg of free base per mL 60 to 80 percent of lidocaine hydrochloride is protein bound. Binding is also dependent on the plasma concentration of the alpha-1-acid glycoprotein.
Lidocaine hydrochloride crosses the blood-brain and placental barriers, presumably by passive diffusion.
Lidocaine hydrochloride is metabolized rapidly by the liver, and metabolites and unchanged drug are excreted by the kidneys. Biotransformation includes oxidative N-dealkylation, ring hydroxylation, cleavage of the amide linkage, and conjugation. N-dealkylation, a major pathway of biotransformation, yields the metabolites monoethylglycinexylidide and glycinexylidide. The pharmacological/toxicological actions of these metabolites are similar to, but less potent than, those of lidocaine hydrochloride. Approximately 90% of lidocaine hydrochloride administered is excreted in the form of various metabolites, and less than 10% is excreted unchanged. The primary metabolite in urine is a conjugate of 4-hydroxy-2,6-dimethylaniline.
The elimination half-life of lidocaine hydrochloride following an intravenous bolus injection is typically 1.5 to 2 hours. Because of the rapid rate at which lidocaine hydrochloride is metabolized, any condition that affects liver function may alter lidocaine hydrochloride kinetics. The half-life may be prolonged two-fold or more in patients with liver dysfunction. Renal dysfunction does not affect lidocaine hydrochloride kinetics but may increase the accumulation of metabolites.
Factors such as acidosis and the use of CNS stimulants and depressants affect the CNS levels of lidocaine hydrochloride required to produce overt systemic effects. Objective adverse manifestations become increasingly apparent with increasing venous plasma levels above 6 mcg free base per mL. In the rhesus monkey arterial blood levels of 18 to 21 mcg/mL have been shown to be threshold for convulsive activity.

INDICATIONS AND USAGE

Lidocaine hydrochloride injection is indicated for production of local or regional anesthesia by infiltration techniques such as percutaneous injection and intravenous regional anesthesia by peripheral nerve block techniques such as brachial plexus and intercostal and by central neural techniques such as lumbar and caudal epidural blocks, when the accepted procedures for these techniques as described in standard textbooks are observed.

CONTRAINDICATIONS

Lidocaine hydrochloride is contraindicated in patients with a known history of hypersensitivity to local anesthetics of the amide type.

WARNINGS

LIDOCAINE HYDROCHLORIDE INJECTION FOR INFILTRATION AND NERVE BLOCK SHOULD BE EMPLOYED ONLY BY CLINICIANS WHO ARE WELL VERSED IN DIAGNOSIS AND MANAGEMENT OF DOSE-RELATED TOXICITY AND OTHER ACUTE EMERGENCIES THAT MIGHT ARISE FROM THE BLOCK TO BE EMPLOYED AND THEN ONLY AFTER ENSURING THE IMMEDIATEAVAILABILITY OF OXYGEN, OTHER RESUSCITATIVE DRUGS, CARDIOPULMONARY EQUIPMENT AND THE PERSONNEL NEEDED FOR PROPER MANAGEMENT OF TOXIC REACTIONS AND RELATED EMERGENCIES (see also ADVERSE REACTIONSand PRECAUTIONS). DELAY IN PROPER MANAGEMENT OF DOSE-RELATED TOXICITY, UNDERVENTILATION FROM ANY CAUSE AND/OR ALTERED SENSITIVITY MAY LEAD TO THE DEVELOPMENT OF ACIDOSIS, CARDIAC ARREST AND, POSSIBLY, DEATH.
Methemoglobinemia
Cases of methemoglobinemia have been reported in association with local anesthetic use. Although all patients are at risk for methemoglobinemia, patients with glucose-6-phosphate dehydrogenase deficiency, congenital or idiopathic methemoglobinemia, cardiac or pulmonary compromise, infants under 6 months of age, and concurrent exposure to oxidizing agents or their metabolites are more susceptible to developing clinical manifestations of the condition. If local anesthetics must be used in these patients, close monitoring for symptoms and signs of methemoglobinemia is recommended.
Signs of methemoglobinemia may occur immediately or may be delayed some hours after exposure, and are characterized by a cyanotic skin discoloration and/or abnormal coloration of the blood. Methemoglobin levels may continue to rise; therefore, immediate treatment is required to avert more serious central nervous system and cardiovascular adverse effects, including seizures, coma, arrhythmias, and death. Discontinue lidocaine hydrochloride and any other oxidizing agents. Depending on the severity of the signs and symptoms, patients may respond to supportive care, i.e., oxygen therapy, hydration. A more severe clinical presentation may require treatment with methylene blue, exchange transfusion, or hyperbaric oxygen.
Intra-articular infusions of local anesthetics following arthroscopic and other surgical procedures is an unapproved use, and there have been post-marketing reports of chondrolysis in patients receiving such infusions. The majority of reported cases of chondrolysis have involved the shoulder joint; cases of gleno-humeral chondrolysis have been described in pediatric and adult patients following intra-articular infusions of local anesthetics with and without epinephrine for periods of 48 to 72 hours. There is insufficient information to determine whether shorter infusion periods are not associated with these findings. The time of onset of symptoms, such as joint pain, stiffness and loss of motion can be variable, but may begin as early as the 2ndmonth after surgery. Currently, there is no effective treatment for chondrolysis; patients who experienced chondrolysis have required additional diagnostic and therapeutic procedures and some required arthroplasty or shoulder replacement.
To avoid intravascular injection, aspiration should be performed before the local anesthetic solution is injected. The needle must be repositioned until no return of blood can be elicited by aspiration. Note, however, that the absence of blood in the syringe does not guarantee that intravascular injection has been avoided.
Anaphylactic reactions may occur following administration of lidocaine hydrochloride (see ADVERSE REACTIONS).
In the case of severe reaction, discontinue the use of the drug.

PRECAUTIONS

General

The safety and effectiveness of lidocaine hydrochloride depend on proper dosage, correct technique, adequate precautions, and readiness for emergencies. Standard textbooks should be consulted for specific techniques and precautions for various regional anesthetic procedures.
Resuscitative equipment, oxygen, and other resuscitative drugs should be available for immediate use (see WARNINGSand ADVERSE REACTIONS). The lowest dosage that results in effective anesthesia should be used to avoid high plasma levels and serious adverse effects. Syringe aspirations should also be performed before and during each supplemental injection when using indwelling catheter techniques. During the administration of epidural anesthesia, it is recommended that a test dose be administered initially and that the patient be monitored for central nervous system toxicity and cardiovascular toxicity, as well as for signs of unintended intrathecal administration, before proceeding. When clinical conditions permit, consideration should be given to employing local anesthetic solutions that contain epinephrine for the test dose because circulatory changes compatible with epinephrine may also serve as a warning sign of unintended intravascular injection. An intravascular injection is still possible even if aspirations for blood are negative. Repeated doses of lidocaine hydrochloride may cause significant increases in blood levels with each repeated dose because of slow accumulation of the drug or its metabolites. Tolerance to elevated blood levels varies with the status of the patient. Debilitated, elderly patients, acutely ill patients, and children should be given reduced doses commensurate with their age and physical condition. Lidocaine hydrochloride should also be used with caution in patients with severe shock or heart block.
Lumbar and caudal epidural anesthesia should be used with extreme caution in persons with the following conditions: existing neurological disease, spinal deformities, septicemia, and severe hypertension.
Local anesthetic solutions containing a vasoconstrictor should be used cautiously and in carefully circumscribed quantities in areas of the body supplied by end arteries or having otherwise compromised blood supply. Patients with peripheral vascular disease and those with hypertensive vascular disease may exhibit exaggerated vasoconstrictor response. Ischemic injury or necrosis may result. Preparations containing a vasoconstrictor should be used with caution in patients during or following the administration of potent general anesthetic agents, since cardiac arrhythmias may occur under such conditions.
Careful and constant monitoring of cardiovascular and respiratory (adequacy of ventilation) vital signs and the patient’s state of consciousness should be accomplished after each local anesthetic injection. It should be kept in mind at such times that restlessness, anxiety, tinnitus, dizziness, blurred vision, tremors, depression or drowsiness may be early warning signs of central nervous system toxicity.
Since amide-type local anesthetics are metabolized by the liver, lidocaine hydrochloride injection should be used with caution in patients with hepatic disease. Patients with severe hepatic disease, because of their inability to metabolize local anesthetics normally, are at greater risk of developing toxic plasma concentrations. Lidocaine hydrochloride injection should also be used with caution in patients with impaired cardiovascular function since they may be less able to compensate for functional changes associated with the prolongation of A-V conduction produced by these drugs.
Many drugs used during the conduct of anesthesia are considered potential triggering agents for familial malignant hyperthermia. Since it is not known whether amide-type local anesthetics may trigger this reaction and since the need for supplemental general anesthesia cannot be predicted in advance, it is suggested that a standard protocol for the management of malignant hyperthermia should be available. Early unexplained signs of tachycardia, tachypnea, labile blood pressure and metabolic acidosis may precede temperature elevation. Successful outcome is dependent on early diagnosis, prompt discontinuance of the suspect triggering agent(s) and institution of treatment, including oxygen therapy, indicated supportive measures and dantrolene (consult dantrolene sodium intravenous package insert before using).
Proper tourniquet technique, as described in publications and standard textbooks, is essential in the performance of intravenous regional anesthesia. Solutions containing epinephrine or other vasoconstrictors should not be used for this technique.
Lidocaine hydrochloride should be used with caution in persons with known drug sensitivities. Patients allergic to para-aminobenzoic acid derivatives (procaine, tetracaine, benzocaine, etc.) have not shown cross-sensitivity to lidocaine hydrochloride.

Use in the Head and Neck Area

Small doses of local anesthetics injected into the head and neck area, including retrobulbar, dental and stellate ganglion blocks, may produce adverse reactions similar to systemic toxicity seen with unintentional intravascular injections of larger doses. Confusion, convulsions, respiratory depression and/or respiratory arrest, and cardiovascular stimulation or depression have been reported. These reactions may be due to intra-arterial injection of the local anesthetic with retrograde flow to the cerebral circulation. Patients receiving these blocks should have their circulation and respiration monitored and be constantly observed. Resuscitative equipment and personnel for treating adverse reactions should be immediately available. Dosage recommendations should not be exceeded (see DOSAGE AND ADMINISTRATION).

Information for Patients

When appropriate, patients should be informed in advance that they may experience temporary loss of sensation and motor activity, usually in the lower half of the body, following proper administration of epidural anesthesia.
Inform patients that use of local anesthetics may cause methemoglobinemia, a serious condition that must be treated promptly. Advise patients or caregivers to seek immediate medical attention if they or someone in their care experience the following signs or symptoms: pale, gray, or blue colored skin (cyanosis); headache; rapid heart rate; shortness of breath; lightheadedness; or fatigue.

Clinically Significant Drug Interactions

The administration of local anesthetic solutions containing epinephrine or norepinephrine to patients receiving monoamine oxidase inhibitors or tricyclic antidepressants may produce severe, prolonged hypertension.
Phenothiazines and butyrophenones may reduce or reverse the pressor effect of epinephrine.
Concurrent use of these agents should generally be avoided. In situations when concurrent therapy is necessary, careful patient monitoring is essential.
Concurrent administration of vasopressor drugs (for the treatment of hypotension related to obstetric blocks) and ergot-type oxytocic drugs may cause severe, persistent hypertension or cerebrovascular accidents.

Drug/Laboratory Test Interactions

The intramuscular injection of lidocaine hydrochloride may result in an increase in creatine phosphokinase levels. Thus, the use of this enzyme determination, without isoenzyme separation, as a diagnostic test for the presence of acute myocardial infarction may be compromised by the intramuscular injection of lidocaine hydrochloride.
Patients who are administered local anesthetics are at increased risk of developing methemoglobinemia when concurrently exposed to the following drugs, which could include other local anesthetics:

Examples of Drugs Associated with Methemoglobinemia:
Class | Examples
Nitrates/Nitrites | nitric oxide, nitroglycerin, nitroprusside, nitrous oxide
Local anesthetics | articaine, benzocaine, bupivacaine, lidocaine, mepivacaine, prilocaine, procaine, ropivacaine, tetracaine
Antineoplastic agents | cyclophosphamide, flutamide, hydroxyurea, ifosfamide, rasburicase
Antibiotics | dapsone, nitrofurantoin, para-aminosalicylic acid, sulfonamides
Antimalarials | chloroquine, primaquine
Anticonvulsants | Phenobarbital, phenytoin, sodium valproate
Other drugs | acetaminophen, metoclopramide, quinine, sulfasalazine

Carcinogenesis, Mutagenesis, Impairment of Fertility

Studies of lidocaine hydrochloride in animals to evaluate the carcinogenic and mutagenic potential or the effect on fertility have not been conducted.

Pregnancy

Teratogenic Effects

Reproduction studies have been performed in rats at doses up to 6.6 times the human dose and have revealed no evidence of harm to the fetus caused by lidocaine hydrochloride. There are, however, no adequate and well-controlled studies in pregnant women. Animal reproduction studies are not always predictive of human response. General consideration should be given to this fact before administering lidocaine hydrochloride to women of childbearing potential, especially during early pregnancy when maximum organogenesis takes place.

Labor and Delivery

Local anesthetics rapidly cross the placenta and when used for epidural, paracervical, pudendal or caudal block anesthesia, can cause varying degrees of maternal, fetal and neonatal toxicity (see CLINICAL PHARMACOLOGY, Pharmacokinetics and Metabolism). The potential for toxicity depends upon the procedure performed, the type and amount of drug used, and the technique of drug administration. Adverse reactions in the parturient, fetus and neonate involve alterations of the central nervous system, peripheral vascular tone and cardiac function.
Maternal hypotension has resulted from regional anesthesia. Local anesthetics produce vasodilation by blocking sympathetic nerves. Elevating the patient’s legs and positioning her on her left side will help prevent decreases in blood pressure.
The fetal heart rate also should be monitored continuously, and electronic fetal monitoring is highly advisable.
Epidural, spinal, paracervical, or pudendal anesthesia may alter the forces of parturition through changes in uterine contractility or maternal expulsive efforts. In one study, paracervical block anesthesia was associated with a decrease in the mean duration of first stage labor and facilitation of cervical dilation. However, spinal and epidural anesthesia have also been reported to prolong the second stage of labor by removing the parturient’s reflex urge to bear down or by interfering with motor function. The use of obstetrical anesthesia may increase the need for forceps assistance.
The use of some local anesthetic drug products during labor and delivery may be followed by diminished muscle strength and tone for the first day or two of life. The long-term significance of these observations is unknown. Fetal bradycardia may occur in 20 to 30 percent of patients receiving paracervical nerve block anesthesia with the amide-type local anesthetics and may be associated with fetal acidosis. Fetal heart rate should always be monitored during paracervical anesthesia. The physician should weigh the possible advantages against risks when considering a paracervical block in prematurity, toxemia of pregnancy, and fetal distress. Careful adherence to recommended dosage is of the utmost importance in obstetrical paracervical block. Failure to achieve adequate analgesia with recommended doses should arouse suspicion of intravascular or fetal intracranial injection. Cases compatible with unintended fetal intracranial injection of local anesthetic solution have been reported following intended paracervical or pudendal block or both. Babies so affected present with unexplained neonatal depression at birth, which correlates with high local anesthetic serum levels, and often manifest seizures within six hours. Prompt use of supportive measures combined with forced urinary excretion of the local anesthetic has been used successfully to manage this complication.
Case reports of maternal convulsions and cardiovascular collapse following use of some local anesthetics for paracervical block in early pregnancy (as anesthesia for elective abortion) suggest that systemic absorption under these circumstances may be rapid. The recommended maximum dose of each drug should not be exceeded. Injection should be made slowly and with frequent aspiration. Allow a 5-minute interval between sides.

Nursing Mothers

It is not known whether this drug is excreted in human milk. Because many drugs are excreted in human milk, caution should be exercised when lidocaine hydrochloride is administered to a nursing woman.

Pediatric Use

Dosages in children should be reduced, commensurate with age, body weight and physical condition, see DOSAGE AND ADMINISTRATION.

ADVERSE REACTIONS

Systemic

Adverse experiences following the administration of lidocaine hydrochloride are similar in nature to those observed with other amide local anesthetic agents. These adverse experiences are, in general, dose-related and may result from high plasma levels caused by excessive dosage, rapid absorption or inadvertent intravascular injection, or may result from a hypersensitivity, idiosyncrasy or diminished tolerance on the part of the patient. Serious adverse experiences are generally systemic in nature. The following types are those most commonly reported:

Central Nervous System

CNS manifestations are excitatory and/or depressant and may be characterized by lightheadedness, nervousness, apprehension, euphoria, confusion, dizziness, drowsiness, tinnitus, blurred or double vision, vomiting, sensations of heat, cold or numbness, twitching, tremors, convulsions, unconsciousness, respiratory depression and arrest. The excitatory manifestations may be very brief or may not occur at all, in which case the first manifestation of toxicity may be drowsiness merging into unconsciousness and respiratory arrest.

Drowsiness following the administration of lidocaine hydrochloride is usually an early sign of a high blood level of the drug and may occur as a consequence of rapid absorption.

Cardiovascular System

Cardiovascular manifestations are usually depressant and are characterized by bradycardia, hypotension, and cardiovascular collapse, which may lead to cardiac arrest.

Allergic

Allergic reactions are characterized by cutaneous lesions, urticaria, edema or anaphylactoid reactions. Allergic reactions may occur as a result of sensitivity to local anesthetic agents. Allergic reactions, including anaphylactic reactions, may occur as a result of sensitivity to lidocaine, but are infrequent. If allergic reactions do occur, they should be managed by conventional means. The detection of sensitivity by skin testing is of doubtful value.
There have been no reports of cross sensitivity between lidocaine hydrochloride and procainamide or between lidocaine hydrochloride and quinidine.

Neurologic

The incidences of adverse reactions associated with the use of local anesthetics may be related to the total dose of local anesthetic administered and are also dependent upon the particular drug used, the route of administration and the physical status of the patient. In a prospective review of 10,440 patients who received lidocaine hydrochloride for spinal anesthesia, the incidences of adverse reactions were reported to be about 3 percent each for positional headaches, hypotension and backache; 2 percent for shivering; and less than 1 percent each for peripheral nerve symptoms, nausea, respiratory inadequacy and double vision. Many of these observations may be related to local anesthetic techniques, with or without a contribution from the local anesthetic.
In the practice of caudal or lumbar epidural block, occasional unintentional penetration of the subarachnoid space by the catheter may occur. Subsequent adverse effects may depend partially on the amount of drug administered subdurally. These may include spinal block of varying magnitude (including total spinal block), hypotension secondary to spinal block, loss of bladder and bowel control, and loss of perineal sensation and sexual function. Persistent motor, sensory and/or autonomic (sphincter control) deficit of some lower spinal segments with slow recovery (several months) or incomplete recovery have been reported in rare instances when caudal or lumbar epidural block has been attempted. Backache and headache have also been noted following use of these anesthetic procedures.
There have been reported cases of permanent injury to extraocular muscles requiring surgical repair following retrobulbar administration.

Hematologic

Methemoglobinemia.

OVERDOSAGE

Acute emergencies from local anesthetics are generally related to high plasma levels encountered during therapeutic use of local anesthetics or to unintended subarachnoid injection of local anesthetic solution (see ADVERSE REACTIONS, WARNINGS, and PRECAUTIONS).

Management of Local Anesthetic Emergencies

The first consideration is prevention, best accomplished by careful and constant monitoring of cardiovascular and respiratory vital signs and the patient’s state of consciousness after each local anesthetic injection. At the first sign of change, oxygen should be administered.
The first step in the management of convulsions, as well as underventilation or apnea due to unintended subarachnoid injection of drug solution, consists of immediate attention to the maintenance of a patent airway and assisted or controlled ventilation with oxygen and a delivery system capable of permitting immediate positive airway pressure by mask. Immediately after the institution of these ventilatory measures, the adequacy of the circulation should be evaluated, keeping in mind that drugs used to treat convulsions sometimes depress the circulation when administered intravenously. Should convulsions persist despite adequate respiratory support, and if the status of the circulation permits, small increments of an ultra-short acting barbiturate (such as thiopental or thiamylal) or a benzodiazepine (such as diazepam) may be administered intravenously. The clinician should be familiar, prior to the use of local anesthetics, with these anticonvulsant drugs. Supportive treatment of circulatory depression may require administration of intravenous fluids and, when appropriate, a vasopressor as directed by the clinical situation (e.g., ephedrine).
If not treated immediately, both convulsions and cardiovascular depression can result in hypoxia, acidosis, bradycardia, arrhythmias and cardiac arrest. Underventilation or apnea due to unintentional subarachnoid injection of local anesthetic solution may produce these same signs and also lead to cardiac arrest if ventilatory support is not instituted. If cardiac arrest should occur, standard cardiopulmonary resuscitative measures should be instituted.
Endotracheal intubation, employing drugs and techniques familiar to the clinician, may be indicated, after initial administration of oxygen by mask, if difficulty is encountered in the maintenance of a patent airway or if prolonged ventilatory support (assisted or controlled) is indicated.
Dialysis is of negligible value in the treatment of acute overdosage with lidocaine hydrochloride.
The oral LD50of lidocaine hydrochloride in non-fasted female rats is 459 (346 to 773) mg/kg (as the salt) and 214 (159 to 324) mg/kg (as the salt) in fasted female rats.

DOSAGE AND ADMINISTRATION

Table 1 (Recommended Dosages) summarizes the recommended volumes and concentrations of lidocaine hydrochloride injection for various types of anesthetic procedures. The dosages suggested in this table are for normal healthy adults and refer to the use of epinephrine-free solutions. When larger volumes are required, only solutions containing epinephrine should be used except in those cases where vasopressor drugs may be contraindicated.
There have been adverse event reports of chondrolysis in patients receiving intra-articular infusions of local anesthetics following arthroscopic and other surgical procedures. Lidocaine hydrochloride injection is not approved for this use (see WARNINGSand DOSAGE AND ADMINISTRATION).
These recommended doses serve only as a guide to the amount of anesthetic required for most routine procedures. The actual volumes and concentrations to be used depend on a number of factors such as type and extent of surgical procedure, depth of anesthesia and degree of muscular relaxation required, duration of anesthesia required, and the physical condition of the patient. In all cases the lowest concentration and smallest dose that will produce the desired result should be given. Dosages should be reduced for children and for the elderly and debilitated patients and patients with cardiac and/or liver disease.
The onset of anesthesia, the duration of anesthesia and the degree of muscular relaxation are proportional to the volume and concentration (i.e., total dose) of local anesthetic used. Thus, an increase in volume and concentration of lidocaine hydrochloride injection will decrease the onset of anesthesia, prolong the duration of anesthesia, provide a greater degree of muscular relaxation and increase the segmental spread of anesthesia. However, increasing the volume and concentration of lidocaine hydrochloride injection may result in a more profound fall in blood pressure when used in epidural anesthesia. Although the incidence of side effects with lidocaine hydrochloride is quite low, caution should be exercised when employing large volumes and concentrations, since the incidence of side effects is directly proportional to the total dose of local anesthetic agent injected.

Epidural Anesthesia

For epidural anesthesia the following dosage form of lidocaine hydrochloride injection is recommended:
1% without epinephrine 30 mL single dose vials
Although this solution is intended specifically for epidural anesthesia, it may also be used for infiltration and peripheral nerve block, provided it is employed as a single dose unit.
This solution contains no bacteriostatic agent.
In epidural anesthesia, the dosage varies with the number of dermatomes to be anesthetized (generally 2 to 3 mL of the indicated concentration per dermatome).

Caudal and Lumbar Epidural Block

As a precaution against the adverse experience sometimes observed following unintentional penetration of the subarachnoid space, a test dose such as 2 to 3 mL of 1.5% lidocaine hydrochloride should be administered at least 5 minutes prior to injecting the total volume required for a lumbar or caudal epidural block. The test dose should be repeated if the patient is moved in a manner that may have displaced the catheter. Epinephrine, if contained in the test dose (10 to 15 mcg have been suggested), may serve as a warning of unintentional intravascular injection. If injected into a blood vessel, this amount of epinephrine is likely to produce a transient “epinephrine response” within 45 seconds, consisting of an increase in heart rate and systolic blood pressure, circumoral pallor, palpitations and nervousness in the unsedated patient. The sedated patient may exhibit only a pulse rate increase of 20 or more beats per minute for 15 or more seconds. Patients on beta blockers may not manifest changes in heart rate, but blood pressure monitoring can detect an evanescent rise in systolic blood pressure. Adequate time should be allowed for onset of anesthesia after administration of each test dose. The rapid injection of a large volume of lidocaine hydrochloride injection through the catheter should be avoided, and, when feasible, fractional doses should be administered.
In the event of the known injection of a large volume of local anesthetic solution into the subarachnoid space, after suitable resuscitation and if the catheter is in place, consider attempting the recovery of drug by draining a moderate amount of cerebrospinal fluid (such as 10 mL) through the epidural catheter.

MAXIMUM RECOMMENDED DOSAGES

Adults

For normal healthy adults, the maximum individual dose should not exceed 4.5 mg/kg (2 mg/lb) of body weight, and in general it is recom mended that the max i m um t otal dose does not exceed 300 mg. For continuous epidural or caudal anesthesia, the maximum recommended dosage should not be administered at intervals of less than 90 minutes. When continuous lumbar or caudal epidural anesthesia is used for non-obstetrical procedures, more drug may be administered if required to produce adequate anesthesia.
The maximum recommended dose per 90 minute period of lidocaine hydrochloride for paracervical block in obstetrical patients and non-obstetrical patients is 200 mg total. One half of the total dose is usually administered to each side. Inject slowly, five minutes between sides (see also discussion of paracervical block in PRECAUTIONS).
For intravenous regional anesthesia, the dose administered should not exceed 4 mg/kg in adults.

Children

It is difficult to recommend a maximum dose of any drug for children, since this varies as a function of age and weight. For children over 3 years of age who have a normal lean body mass and normal body development, the maximum dose is determined by the child’s age and weight. For example, in a child of 5 years weighing 50 lbs the dose of lidocaine hydrochloride should not exceed 75 to 100 mg (1.5 to 2 mg/lb). The use of even more dilute solutions (i.e., 0.25 to 0.5%) and total dosages not to exceed 3 mg/kg (1.4 mg/lb) are recommended for induction of intravenous regional anesthesia in children.
In order to guard against systemic toxicity, the lowest effective concentration and lowest effective dose should be used at all times. In some cases it will be necessary to dilute available concentrations with 0.9% sodium chloride injection in order to obtain the required final concentration.
NOTE: Parenteral drug products should be inspected visually for particulate matter and discoloration prior to administration whenever the solution and container permit. Do not use if solution is discolored or contains a precipitate.

Table 1: Recommended Dosages
Procedure | Lidocaine Hydrochloride Injection (without epinephrine)
Procedure | Conc (%) | Vol (mL) | Total Dose (mg)
Infiltration
Percutaneous | 0.5 or 1 | 1 to 60 | 5 to 300
Intravenous regional | 0.5 | 10 to 60 | 50 to 300
Peripheral Nerve Blocks, e.g.,
Brachial | 1.5 | 15 to 20 | 225 to 300
Dental | 2 | 1 to 5 | 20 to 100
Intercostal | 1 | 3 | 30
Paravertebral | 1 | 3 to 5 | 30 to 50
Pudendal (each side) | 1 | 10 | 100
Paracervical
Obstetrical analgesia (each side) | 1 | 10 | 100
Sympathetic Nerve Blocks, e.g.,
Cervical (stellate ganglion) | 1 | 5 | 50
Lumbar | 1 | 5 to 10 | 50 to 100
Central Neural Blocks
Epidural*
Thoracic | 1 | 20 to 30 | 200 to 300
Lumbar
Analgesia | 1 | 25 to 30 | 250 to 300
Anesthesia | 1.5 | 15 to 20 | 225 to 300
 | 2 | 10 to 15 | 200 to 300
Caudal
Obstetrical analgesia | 1 | 20 to 30 | 200 to 300
Surgical anesthesia | 1.5 | 15 to 20 | 225 to 300
*Dose determined by number of dermatomes to be anesthetized (2 to 3 mL/dermatome).

THE ABOVE SUGGESTED CONCENTRATIONS AND VOLUMES SERVE ONLY AS A GUIDE. OTHER VOLUMES AND CONCENTRATIONS MAY BE USED PROVIDED THE TOTAL MAXIMUM RECOMMENDED DOSE IS NOT EXCEEDED.

STERILIZATION, STORAGE AND TECHNICAL PROCEDURES

Disinfecting agents containing heavy metals, which cause release of respective ions (mercury, zinc, copper, etc.) should not be used for skin or mucous membrane disinfection as they have been related to incidents of swelling and edema.

HOW SUPPLIED

Lidocaine Hydrochloride Injection, USP is supplied as follows:
Lidocaine Hydrochloride Injection USP, 1% (10 mg/mL)
5 mL Single Dose Vials in a Carton of 10 NDC 55150-162-05
Sterile, Nonpyrogenic

Discard unused portion
Store at20° to 25°C (68° to 77°F). [See USP Controlled Room Temperature.]
The vial stopper is not made with natural rubber latex.
Distributed by:
AuroMedics Pharma LLC

279 Princeton-Hightstown Rd.
E. Windsor, NJ 08520
Manufactured by:
Aurobindo Pharma Limited

Hyderabad - 500038
India

Distributed by:

Advanced Rx Pharmacy of Tennessee, LLC
Revised: February 2020

Active Ingredient Purpose

Povidone Iodine 10% w/v (9.85% w/w/) Antiseptic

Purpose:

- First aid antiseptic to help prevent skin infection in minor cuts, scrapes and burns.
- For preparation of the skin prior to surgery.
- Helps reduce bacteria that can potentially cause skin infections.

Warnings:

- FOR EXTERNAL USE ONLY

Do not use:

- As a first aid antiseptic for more than 1 week.
- In the eyes.
- Over large areas of the body.

Ask a doctor before use if you have:

- Deep puncture wounds
- Animal bites
- Serious burns

Stop Use:

- If irritation and redness develop
- If condition persists for more than 72 hours, consult a physician.

Keep out of reach of children.If swallowed, get medical help or contact a Poison Control Center.

Directions Povidone iodine:

Tear at notch, remove applicator, use only once.

As a first aid antiseptic

- clean affected area
- apply 1 to 3 times daily
- may be covered with a sterile bandage, if bandaged let dry.

For preoperative patient skin preparation

- clean area
- apply to operative site prior to surgery using the applicator

Other information:

Store at room temperature.

Avoid excessive heat

INDICATIONS AND USAGE

For use as an

- first aid antiseptic
- pre-operative skin preperation

Inactive Ingredients

Inactive ingredients: Citric acid, glycerin, polysorbate 80, sodium citrate USP, sodium phosphate dibasic, water

0.9% Sodium Chloride Injection, USP

Fliptop Plastic Vial

LifeShield®Fliptop Plastic Vial

Preservative-Free

Rx only

DESCRIPTION

This preparation is designed solely for parenteral use only after addition of drugs that require dilution or must be dissolved in an aqueous vehicle prior to injection.

0.9% Sodium Chloride Injection, USP is a sterile, nonpyrogenic, isotonic solution of sodium chloride and water for injection. Each mL contains sodium chloride 9 mg. It contains no bacteriostat, antimicrobial agent or added buffer and is supplied only in single-dose containers to dilute or dissolve drugs for injection. 0.308 mOsmol/mL (calc.). 0.9% Sodium Chloride Injection, USP contains no preservatives. The solution may contain hydrochloric acid and/or sodium hydroxide for pH adjustment. pH 5.3 (4.5 to 7.0).

Sodium Chloride, USP is chemically designated NaCl, a white crystalline compound freely soluble in water.

The glass container is a Type I borosilicate glass and meets the requirements of the powdered glass test according to the USP standards.

CLINICAL PHARMACOLOGY

Sodium chloride in water dissociates to provide sodium (Na^+) and chloride (Cl‾) ions. These ions are normal constituents of the body fluids (principally extracellular) and are essential for maintaining electrolyte balance.

The distribution and excretion of sodium (Na^+) and chloride (Cl‾) are largely under the control of the kidney which maintains a balance between intake and output.

The small volume of fluid and amount of sodium chloride provided by 0.9% Sodium Chloride Injection, USP when used only as an isotonic vehicle for parenteral injection of drugs, is unlikely to exert a significant effect on fluid and electrolyte balance except possibly in neonates and very small infants.

Water is an essential constituent of all body tissues and accounts for approximately 70% of total body weight. Average normal adult daily requirement ranges from two to three liters (1.0 to 1.5 liters each for insensible water loss by perspiration and urine production).

Water balance is maintained by various regulatory mechanisms. Water distribution depends primarily on the concentration of electrolytes in the body compartments and sodium (Na^+) plays a major role in maintaining physiologic equilibrium.

INDICATIONS AND USAGE

This parenteral preparation is indicated only for diluting or dissolving drugs for intravenous, intramuscular or subcutaneous injection, according to instructions of the manufacturer of the drug to be administered.

PRECAUTIONS

Consult the manufacturer's instructions for choice of vehicle, appropriate dilution or volume for dissolving the drugs to be injected, including the route and rate of injection.

Inspect reconstituted (diluted or dissolved) drugs for clarity (if soluble) and freedom from unexpected precipitation or discoloration prior to administration.

Pregnancy:Animal reproduction studies have not been conducted with 0.9% Sodium Chloride Injection, USP. It is also not known whether sodium chloride injection containing additives can cause fetal harm when administered to a pregnant woman or can affect reproduction capacity. Sodium chloride injection containing additives should be given to a pregnant woman only if clearly needed.

Pediatric Use:The safety and effectiveness in the pediatric population are based on the similarity of the clinical conditions of the pediatric and adult populations. In neonates or very small infants the volume of fluid may affect fluid and electrolyte balance.

Drug Interactions

Some drugs for injection may be incompatible in a given vehicle, or when combined in the same vehicle or in a vehicle containing benzyl alcohol. Consult with pharmacist, if available.

Use aseptic technique for single or multiple entry and withdrawal from all containers.

When diluting or dissolving drugs, mix thoroughly and use promptly.

Do not store reconstituted solutions of drugs for injection unless otherwise directed by the manufacturer of the solute.

Do not use unless the solution is clear and seal intact. Do not reuse single-dose containers, discard unused portion.

ADVERSE REACTIONS

Reactions which may occur because of this solution, added drugs or the technique of reconstitution or administration include febrile response, local tenderness, abscess, tissue necrosis or infection at the site of injection, venous thrombosis or phlebitis extending from the site of injection and extravasation.

If an adverse reaction does occur, discontinue the infusion, evaluate the patient, institute appropriate countermeasures, and if possible, retrieve and save the remainder of the unused vehicle for examination.

OVERDOSAGE

Use only as a diluent or solvent. This parenteral preparation is unlikely to pose a threat of carbohydrate, sodium chloride or fluid overload except possibly in neonates or very small infants. In the event these should occur, re-evaluate the patient and institute appropriate corrective measures. See PRECAUTIONSand ADVERSE REACTIONS.

DOSAGE AND ADMINISTRATION

The volume of the preparation to be used for diluting or dissolving any drug for injection, is dependent on the vehicle concentration, dose and route of administration as recommended by the manufacturer. This parenteral should be inspected visually for particulate matter and discoloration prior to administration, whenever solution and container permit.

HOW SUPPLIED

0.9% Sodium Chloride Injection, USP is supplied in the following:

Unit | Concentration
NDC 0409-4888-02 10 mL Single-dose Plastic Fliptop Vials | 0.9% (10 mL)

Store at 20 to 25°C (68 to 77°F) [See USP Controlled Room Temperature.]

LIFESHIELD®is the trademark of ICU Medical, Inc. and is used under license.

Distributed by Hospira, Inc., Lake Forest, IL 60045 USA

LAB-1097-2.0

10/2018

Distributed by:

Advanced Rx Pharmacy of Tennessee, LLC

Sterile Water for Injection, USP

Plastic Vial

Rx only

DESCRIPTION

This preparation is designed solely for parenteral use only after addition of drugs that require dilution or must be dissolved in an aqueous vehicle prior to injection.

Sterile Water for Injection, USP is a sterile, nonpyrogenic preparation of water for injection which contains no bacteriostat, antimicrobial agent or added buffer and is supplied only in single-dose containers to dilute or dissolve drugs for injection. For I.V. injection, add sufficient solute to make an approximately isotonic solution.

Water for Injection, USP is chemically designated H2O.

The semi-rigid vial is fabricated from a specially formulated polyolefin. It is a copolymer of ethylene and propylene. The safety of the plastic has been confirmed by tests in animals according to USP biological standards for plastic containers. The container requires no vapor barrier to maintain the proper labeled volume.

CLINICAL PHARMACOLOGY

Water is an essential constituent of all body tissues and accounts for approximately 70% of total body weight. Average normal adult daily requirement ranges from two to three liters (1.0 to 1.5 liters each for insensible water loss by perspiration and urine production).

Water balance is maintained by various regulatory mechanisms. Water for distribution depends primarily on the concentration of electrolytes in the body compartments and sodium (Na^+) plays a major role in maintaining physiologic equilibrium.

The small volume of fluid provided by Sterile Water for Injection, USP when used only as a pharmaceutic aid for diluting or dissolving drugs for parenteral injection, is unlikely to exert a significant effect on fluid balance except possibly in neonates or very small infants.

INDICATIONS AND USAGE

This parenteral preparation is indicated only for diluting or dissolving drugs for intravenous, intramuscular or subcutaneous injection, according to instructions of the manufacturer of the drug to be administered.

CONTRAINDICATIONS

Sterile Water for Injection, USP must be made approximately isotonic prior to use.

WARNINGS

Intravenous administration of Sterile Water for Injection without a solute may result in hemolysis.

PRECAUTIONS

Do not use for intravenous injection unless the osmolar concentration of additives results in an approximate isotonic admixture.

Consult the manufacturer's instructions for choice of vehicle, appropriate dilution or volume for dissolving the drugs to be injected, including the route and rate of injection.

Inspect reconstituted (diluted or dissolved) drugs for clarity (if soluble) and freedom from unexpected precipitation or discoloration prior to administration.

Pregnancy:Animal reproduction studies have not been conducted with Sterile Water for Injection. It is also not known whether sterile water containing additives can cause fetal harm when administered to a pregnant woman or can affect reproduction capacity. Sterile Water for Injection with additives should be given to a pregnant woman only if clearly needed.

Pediatric Use

Safety and effectiveness have been established in pediatric patients. However, in neonates or very small infants the volume of fluid may affect fluid and electrolyte balance.

Drug Interactions

Some drugs for injection may be incompatible in a given vehicle, or when combined in the same vehicle or in a vehicle containing benzyl alcohol. Consult with pharmacist, if available.

Use aseptic technique for single or multiple entry and withdrawal from all containers.

When diluting or dissolving drugs, mix thoroughly and use promptly.

Do not store reconstituted solutions of drugs for injection unless otherwise directed by the manufacturer of the solute.

Do not use unless the solution is clear and seal intact. Do not reuse single-dose containers. Discard unused portion.

ADVERSE REACTIONS

Reactions which may occur because of this solution, added drugs or the technique of reconstitution or administration include febrile response, local tenderness, abscess, tissue necrosis or infection at the site of injection, venous thrombosis or phlebitis extending from the site of injection and extravasation.

If an adverse reaction does occur, discontinue the infusion, evaluate the patient, institute appropriate countermeasures, and if possible, retrieve and save the remainder of the unused vehicle for examination.

OVERDOSAGE

Use only as a diluent or solvent. This parenteral preparation is unlikely to pose a threat of fluid overload except possibly in neonates or very small infants. In the event these should occur, re-evaluate the patient and institute appropriate corrective measures. See WARNINGS, PRECAUTIONSand ADVERSE REACTIONS.

DOSAGE AND ADMINISTRATION

The volume of the preparation to be used for diluting or dissolving any drug for injection is dependent on the vehicle concentration, dose and route of administration as recommended by the manufacturer.

This parenteral should be inspected visually for particulate matter and discoloration prior to administration, whenever solution and container permit.

HOW SUPPLIED

Sterile Water for Injection, USP is supplied in the following:

Unit | Total Content
NDC 0409-4887-17 1 Plastic Fliptop Vials | 10 mL

Store at 20 to 25°C (68 to 77°F). [See USP Controlled Room Temperature.]

Distributed by Hospira, Inc., Lake Forest, IL 60045 USA

LAB-1292-1.0

Revised: 05/2018

Distributed by:

Advanced Rx Pharmacy of Tennessee, LLC

Active ingredient

Isopropyl Alcohol 70% v/v

Purpose

Antiseptic

Uses

For first aid to decrease germs in

- minor cuts
- scrapes
- burns

For preparation of the skin prior to injection

Warnings

For external use only

Flammable - keep away from fire or flame

Do not use

with electrocautery procedures

When using this product do not

- get into eyes
- apply over large areas of the body
- in case of deep or puncture wounds, animal bites or serious burns consult a doctor

Stop use and ask a doctor if

- condition persists or gets worse or lasts for more than 72 hours
- do not use longer than 1 week unless directed by a doctor

Keep out of reach of children.

If swallowed, get medical help or contact a Poison Control Center right away.

Directions

- apply to skin as needed
- discard after single use

Other information

Protect from freezing and avoid excessive heat

Inactive ingredient

Water

PACKAGE LABEL

PRINCIPAL DISPLAY PANEL

NDC: 80425-0349-01

Rx Only

Dyural-80

Kit Contains

1 MethylPREDNISolone Acetate Injec table Suspension, USP 80mg/mL Single Dose Vial (1mL)

1 Bupivacaine HCl 0.25% Single Dose Vial (10mL)

1 Lidocaine HCl Injection, USP 1% Single Dose Vial (5mL)

1 Sterile Water for Inj., USP (10mL)

1 0.9% Sodium Chloride Inj., USP (10mL)

1 Povidone-Iodine Swabsticks (3 Swabs)

5 Isopropyl Alcohol 70% Prep Pads

1 Pair Nitrile Powder Free Sterile Gloves (M)

1 Drape with Fenestration

1 Adhesive Bandage

5 Non Sterile 4x4 Gauze

Needles and Syringes Not Included

1 Dose

Single Use Only

Distributed by:

Advanced Rx Pharmacy of Tennessee, LLC